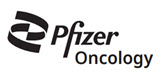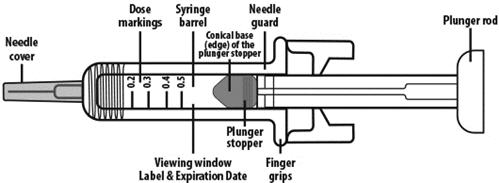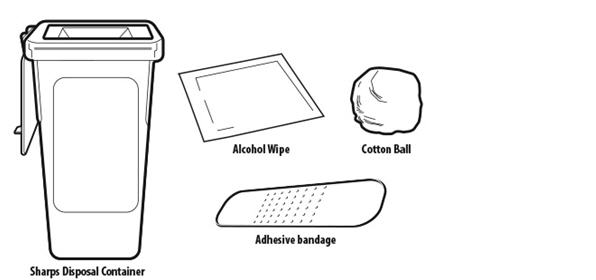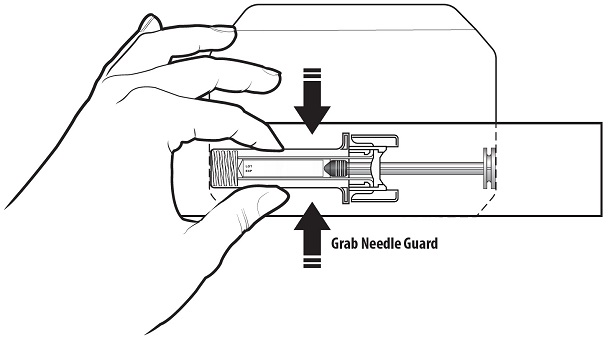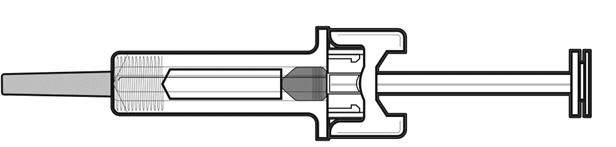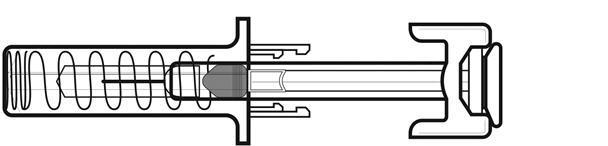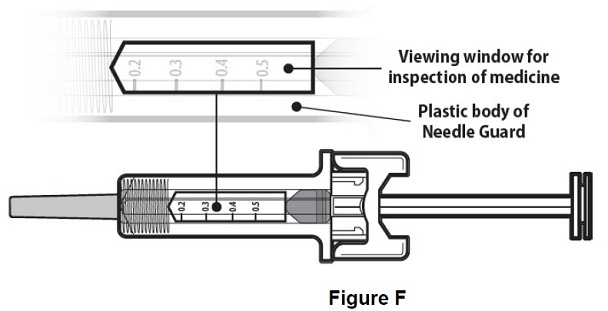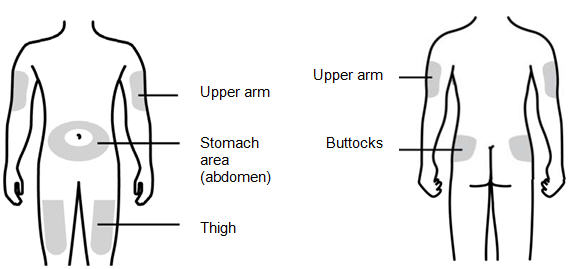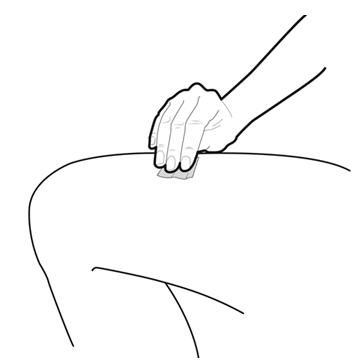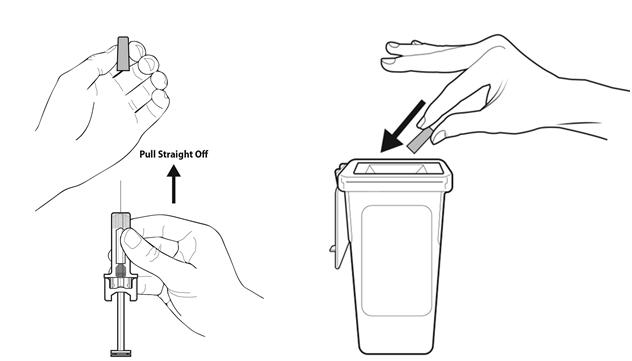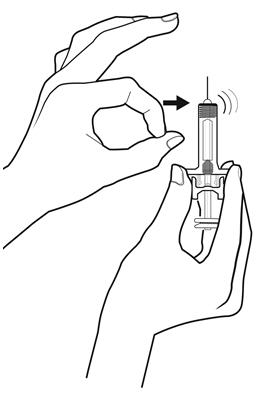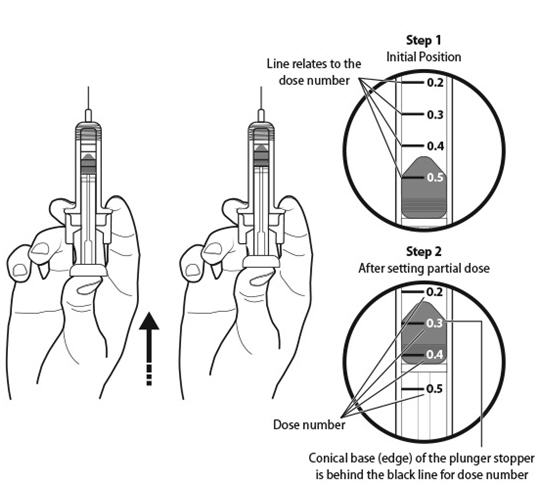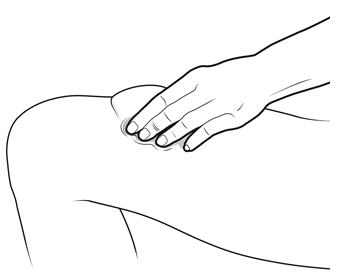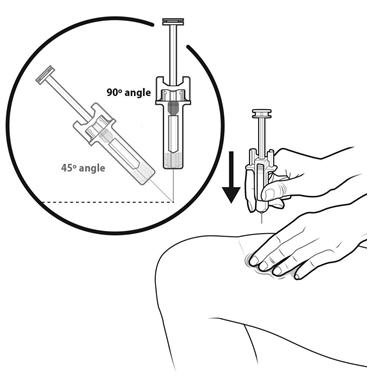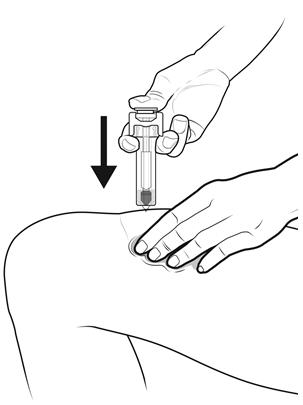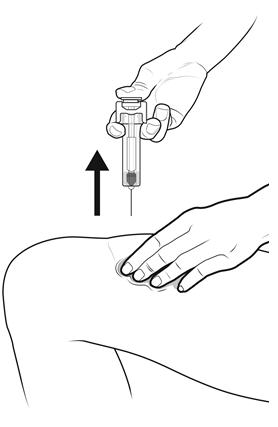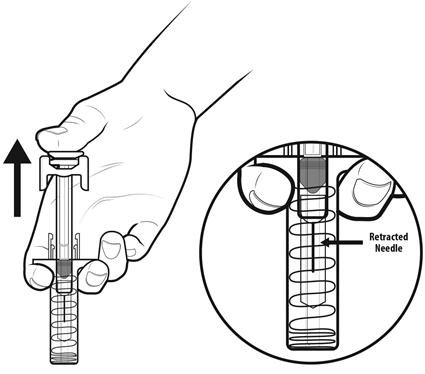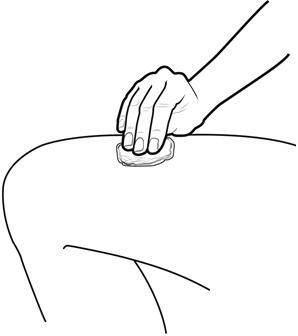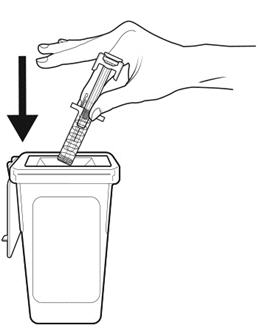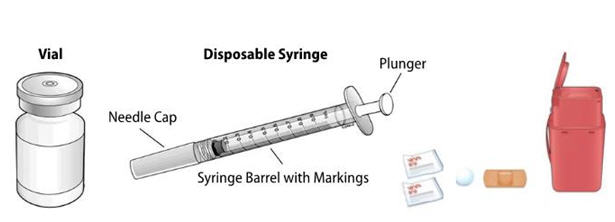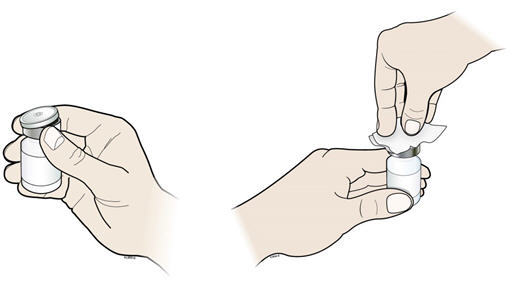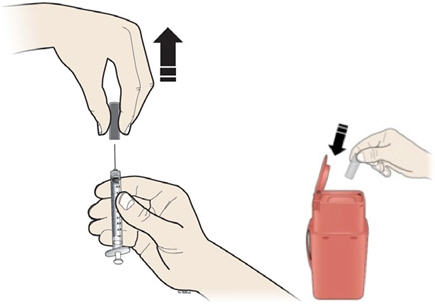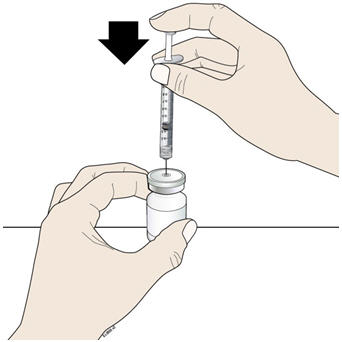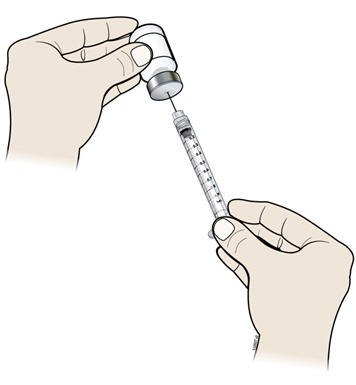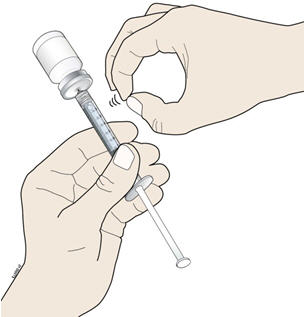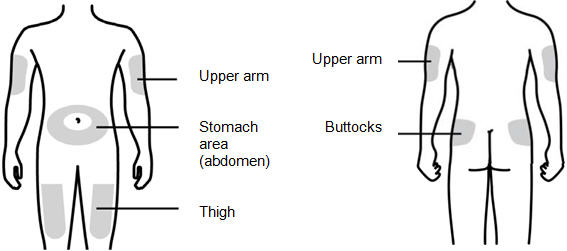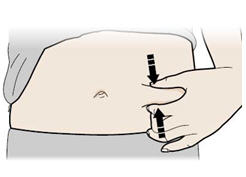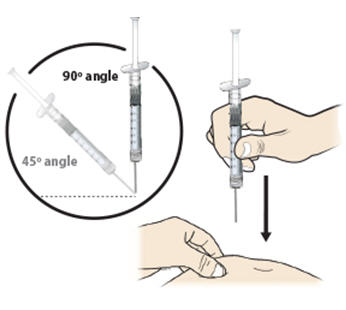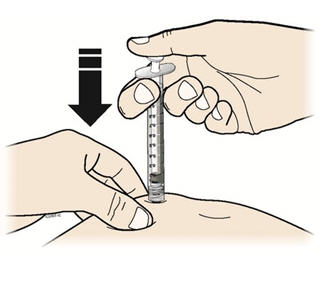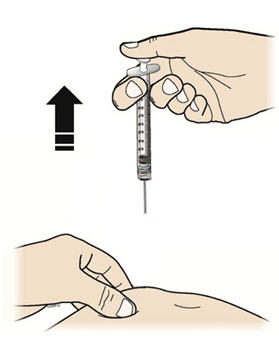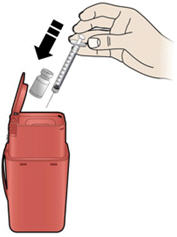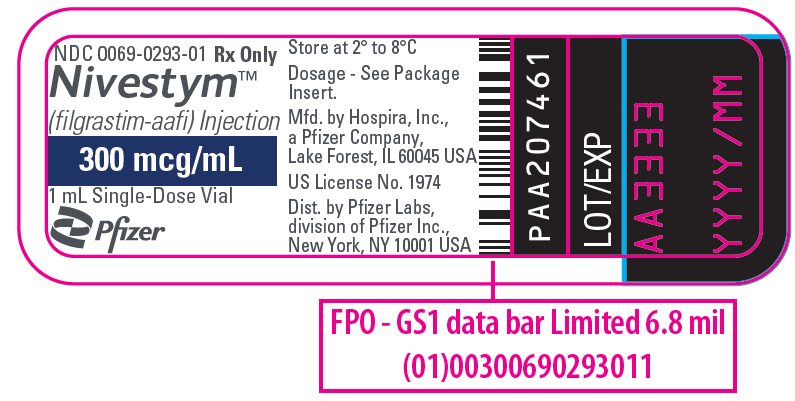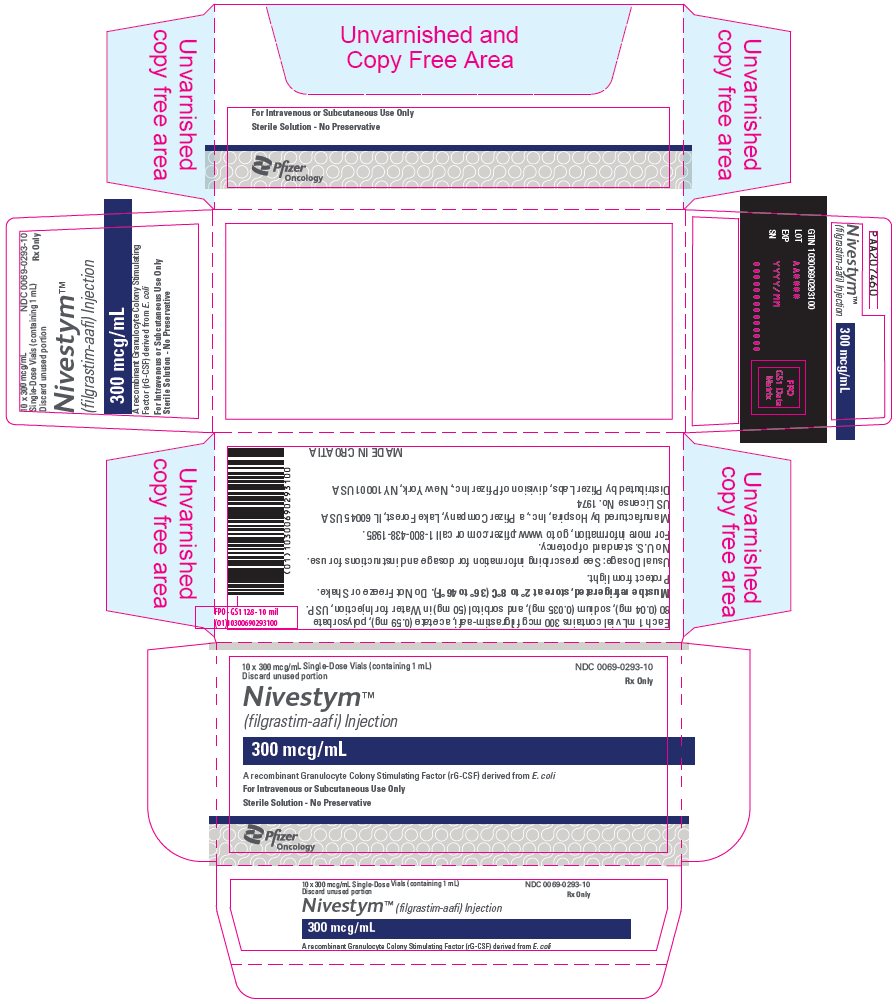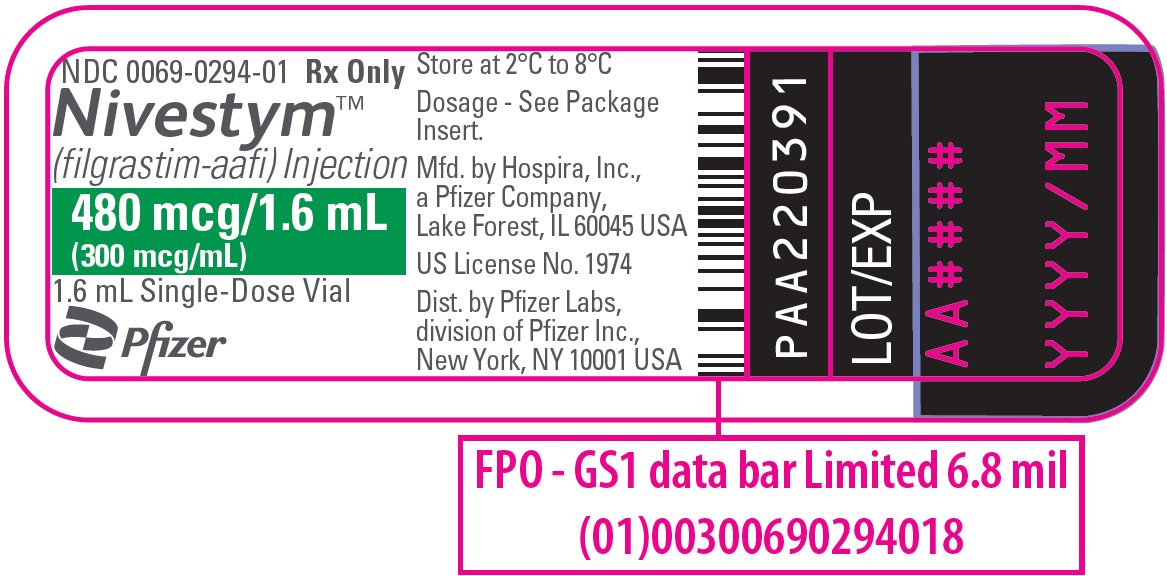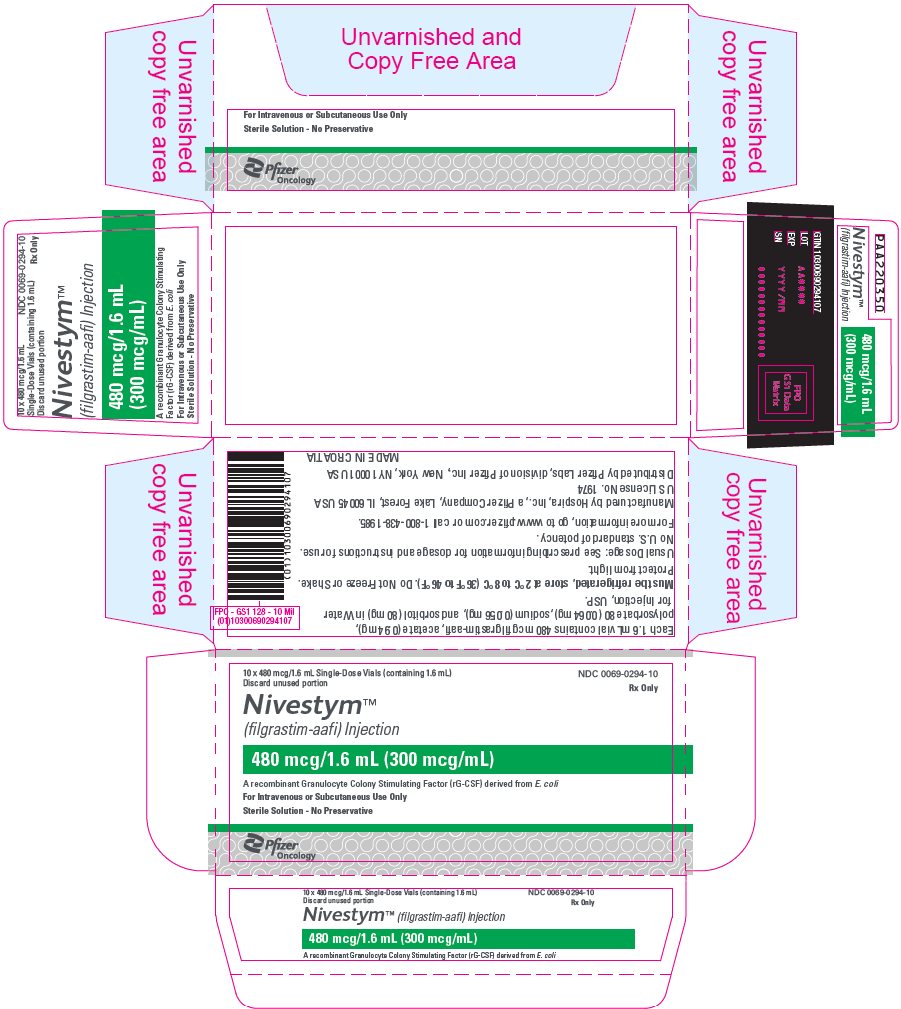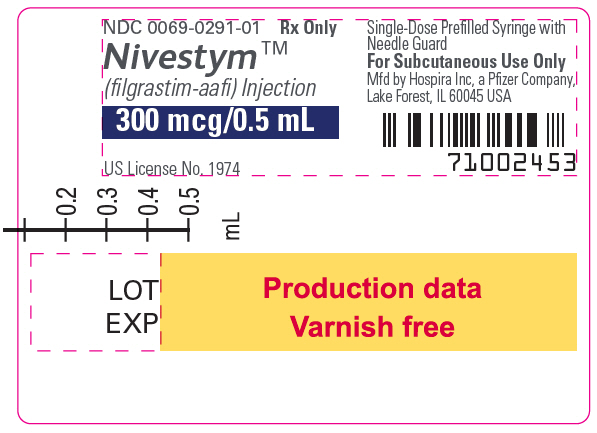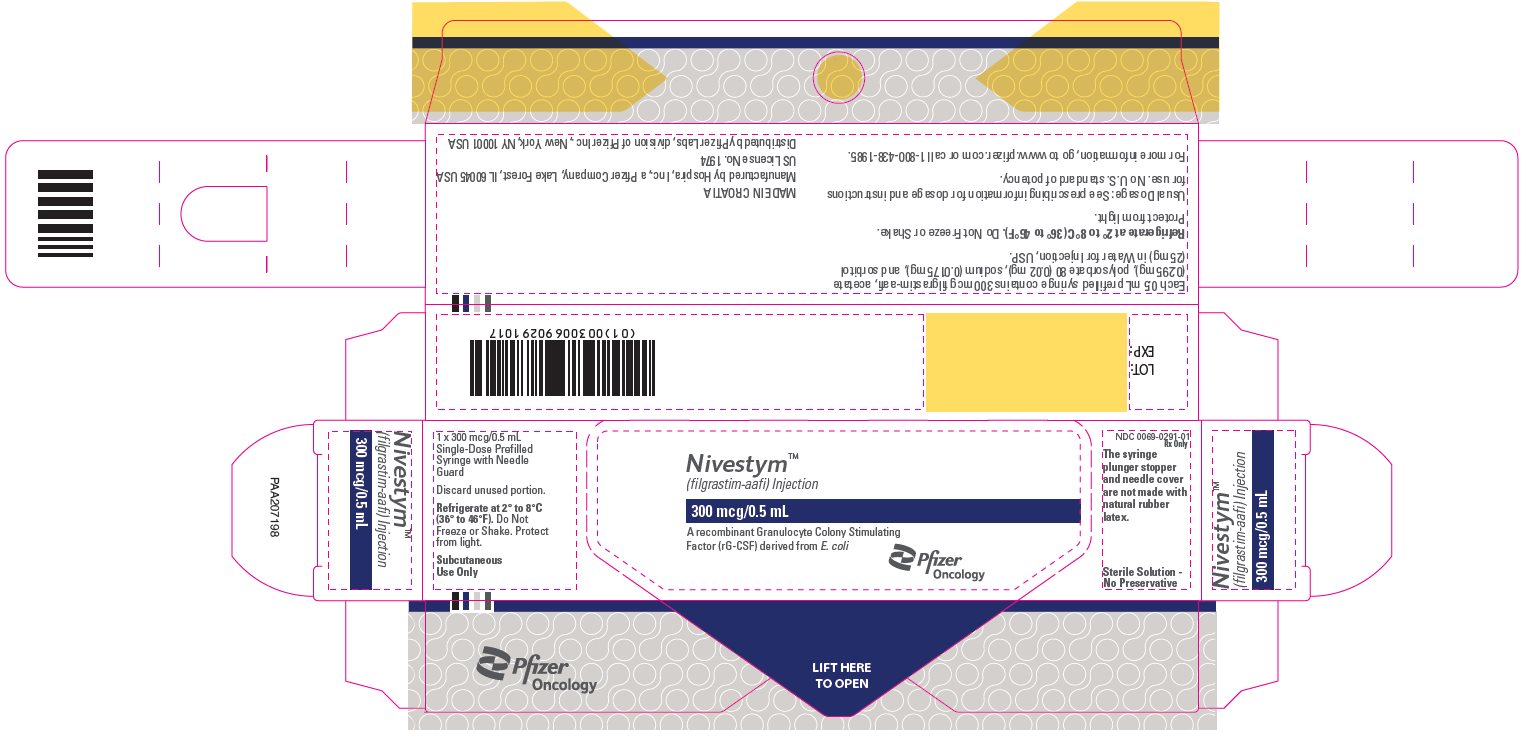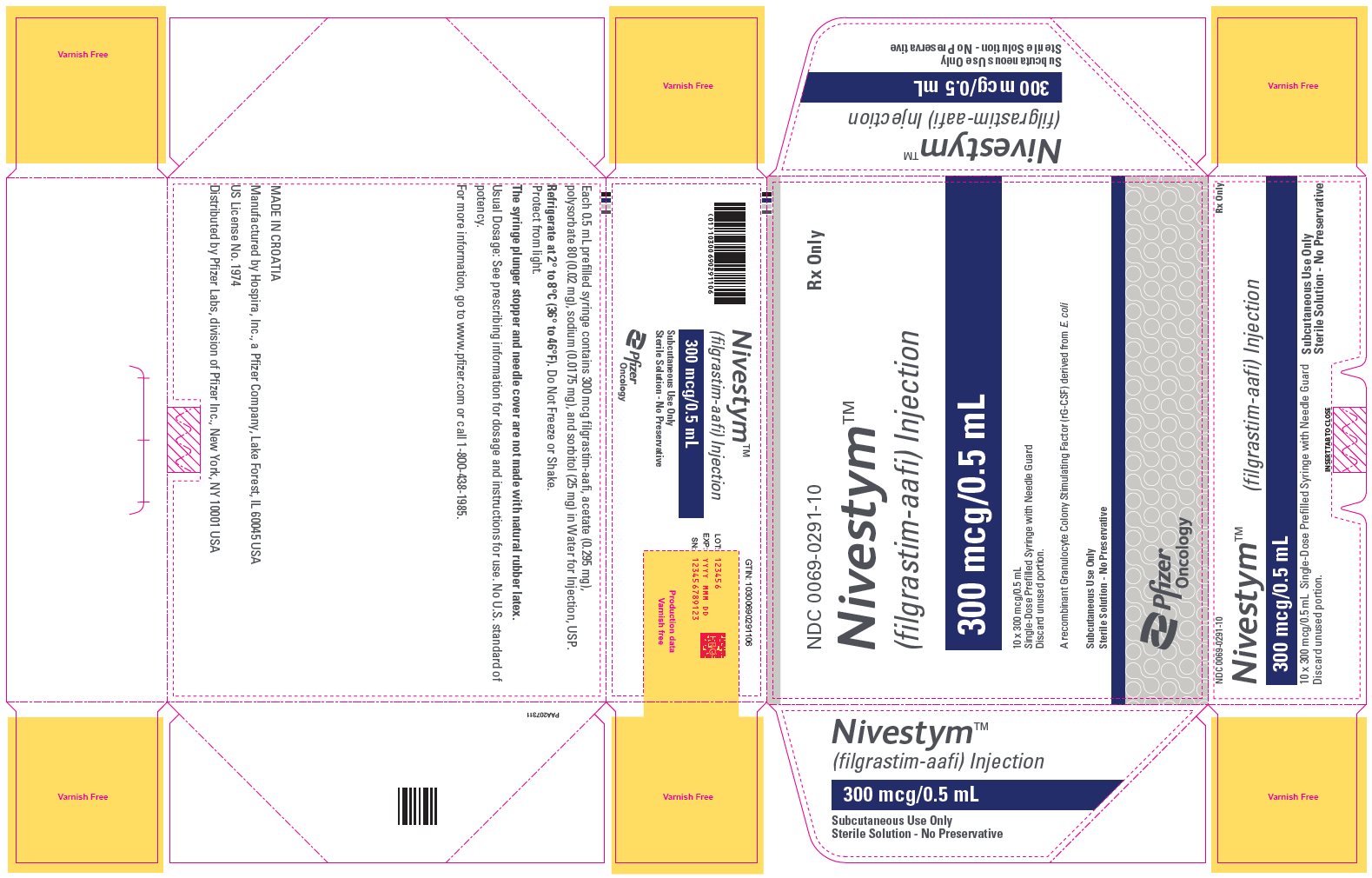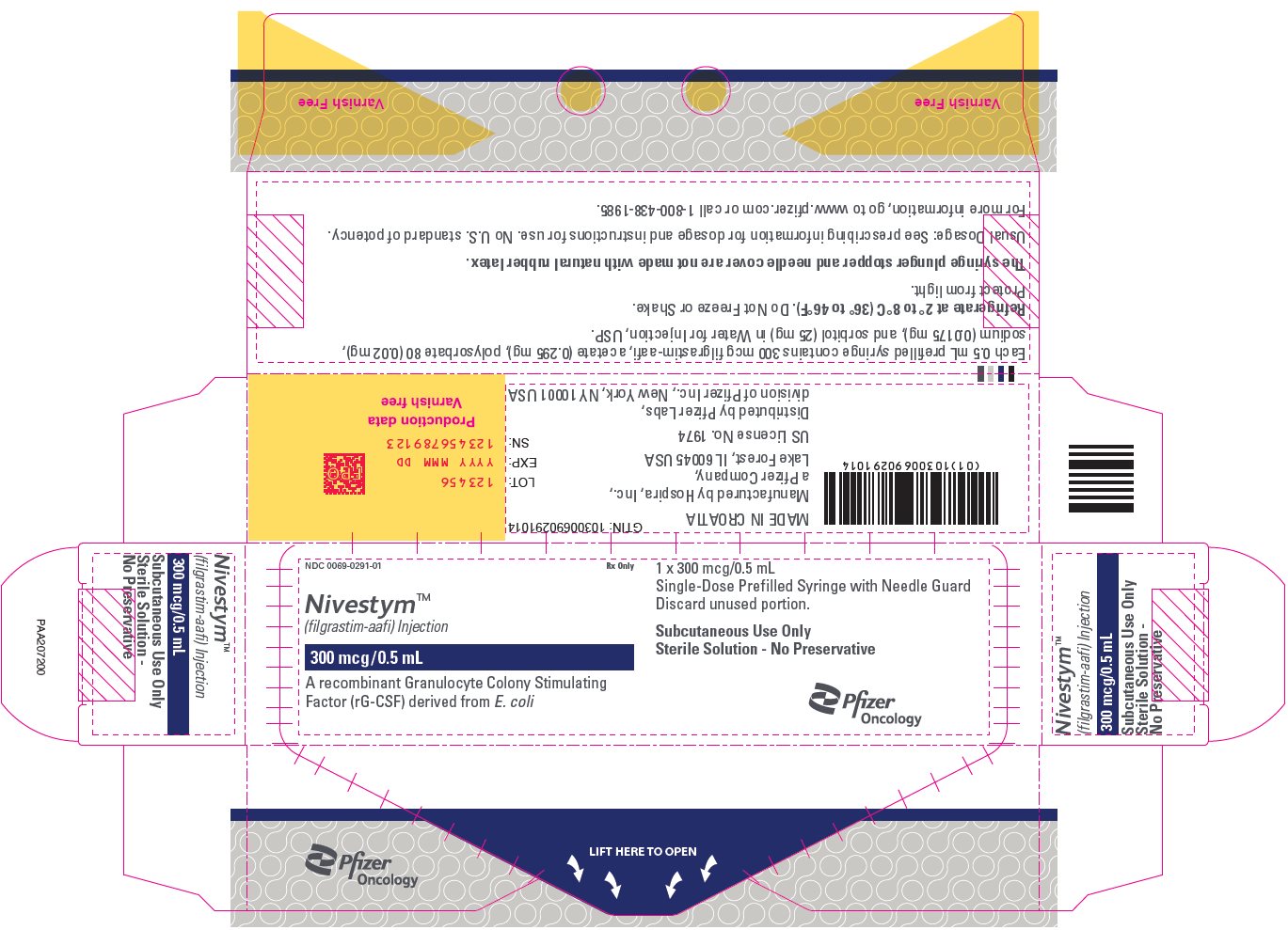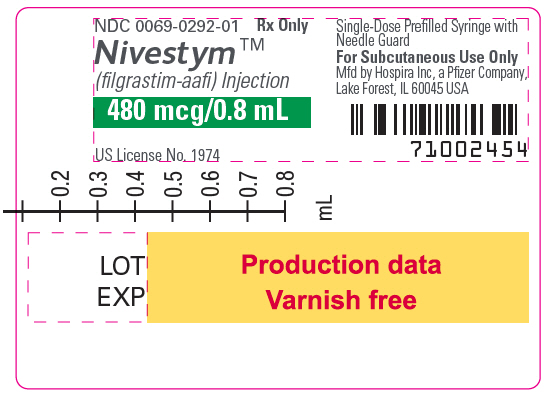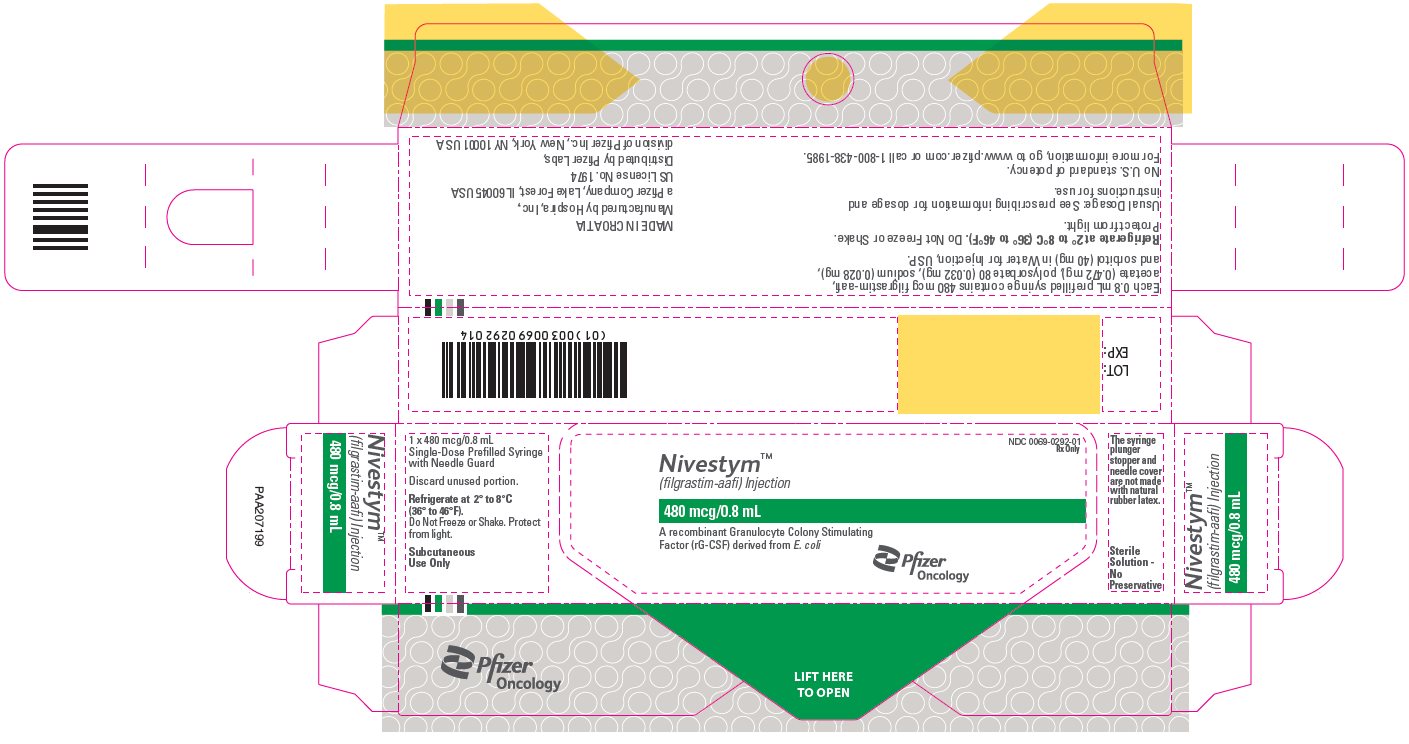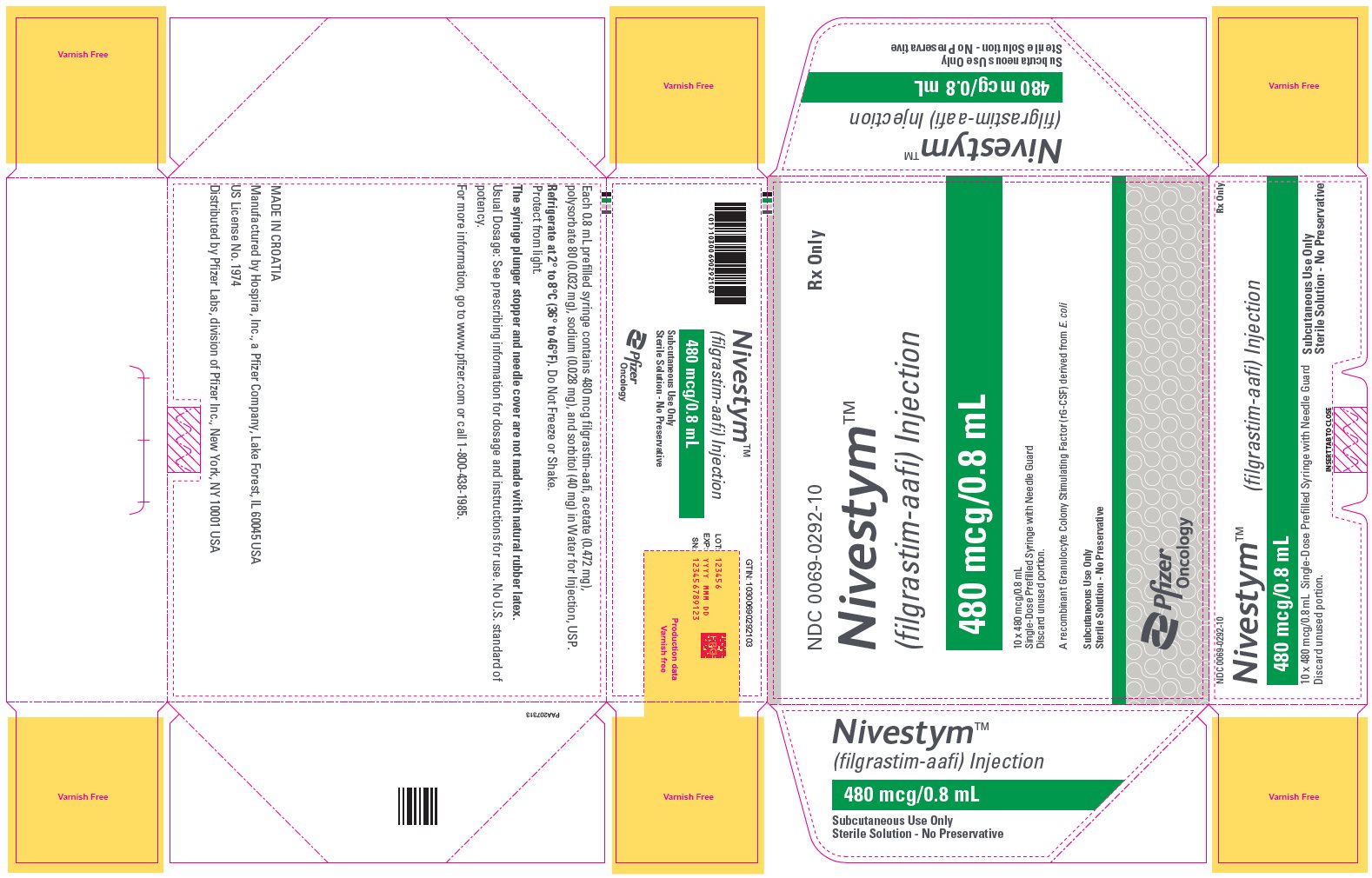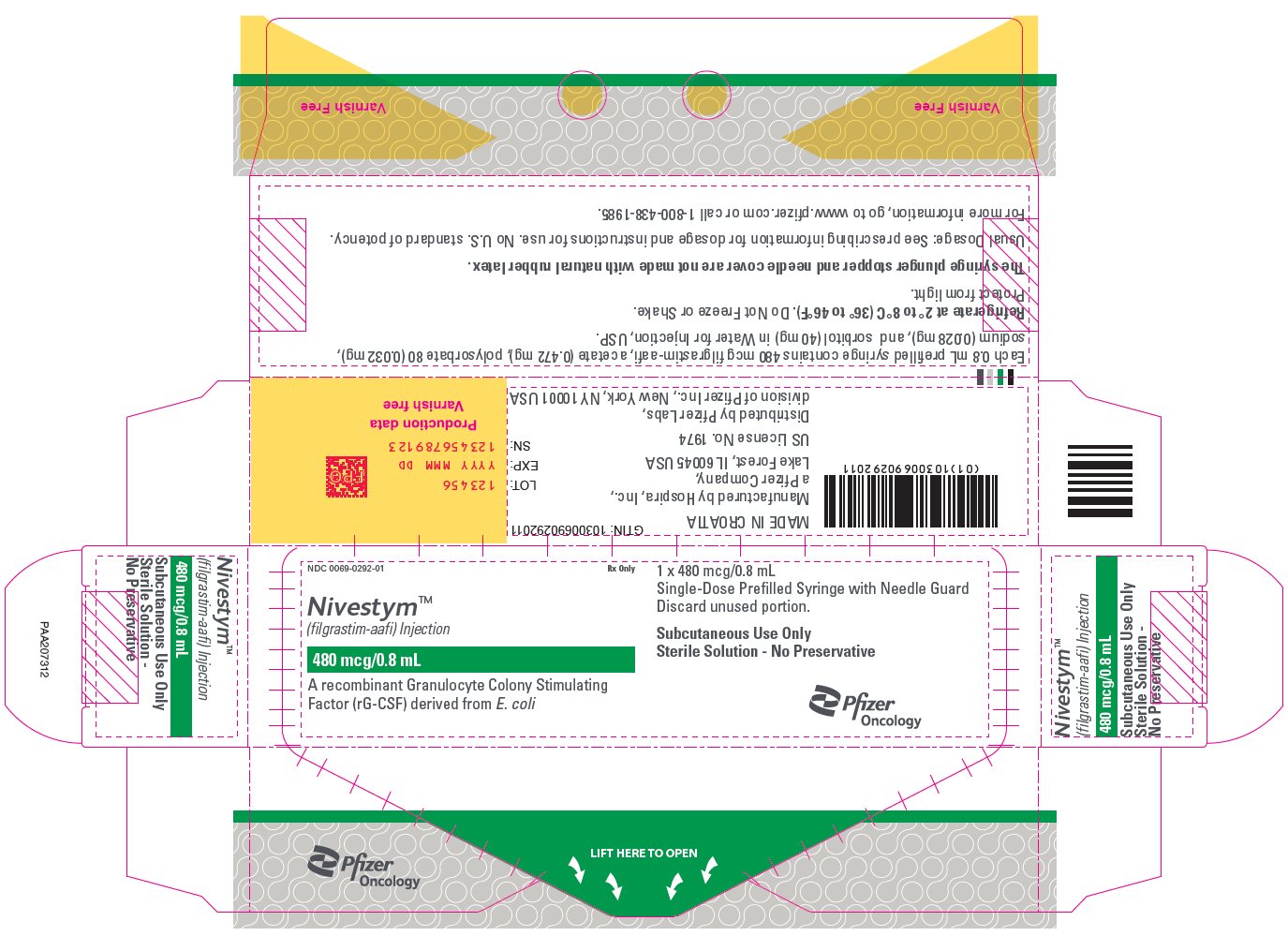 DRUG LABEL: Nivestym
NDC: 0069-0293 | Form: INJECTION, SOLUTION
Manufacturer: Pfizer Laboratories Div Pfizer Inc
Category: prescription | Type: HUMAN PRESCRIPTION DRUG LABEL
Date: 20250812

ACTIVE INGREDIENTS: FILGRASTIM 300 ug/1 mL
INACTIVE INGREDIENTS: POLYSORBATE 80 0.04 mg/1 mL; SORBITOL 50 mg/1 mL; SODIUM ACETATE; WATER

HIGHLIGHTS OF PRESCRIBING INFORMATION

These highlights do not include all the information needed to use NIVESTYM safely and effectively. See full prescribing information for NIVESTYM.
NIVESTYM™ (filgrastim-aafi) injection, for subcutaneous or intravenous use
Initial U.S. Approval: 2018
NIVESTYM (filgrastim-aafi) is biosimilar [Biosimilar means that the biological product is approved based on data demonstrating that it is highly similar to an FDA-approved biological product, known as a reference product, and that there are no clinically meaningful differences between the biosimilar product and the reference product. Biosimilarity of NIVESTYM has been demonstrated for the condition(s) of use (e.g. indication(s), dosing regimen(s)), strength(s), dosage form(s), and route(s) of administration described in its Full Prescribing Information.] to NEUPOGEN (filgrastim).

1 INDICATIONS AND USAGE

NIVESTYM is a leukocyte growth factor indicated to

- Decrease the incidence of infection‚ as manifested by febrile neutropenia‚ in patients with nonmyeloid malignancies receiving myelosuppressive anti-cancer drugs associated with a significant incidence of severe neutropenia with fever. (1.1)
- Reduce the time to neutrophil recovery and the duration of fever, following induction or consolidation chemotherapy treatment of patients with acute myeloid leukemia (AML). (1.2)
- Reduce the duration of neutropenia and neutropenia-related clinical sequelae‚ e.g.‚ febrile neutropenia, in patients with nonmyeloid malignancies undergoing myeloablative chemotherapy followed by bone marrow transplantation (BMT). (1.3)
- Mobilize autologous hematopoietic progenitor cells into the peripheral blood for collection by leukapheresis. (1.4)
- Reduce the incidence and duration of sequelae of severe neutropenia (e.g.‚ fever‚ infections‚ oropharyngeal ulcers) in symptomatic patients with congenital neutropenia‚ cyclic neutropenia‚ or idiopathic neutropenia. (1.5)

2 DOSAGE AND ADMINISTRATION

- Patients with cancer receiving myelosuppressive chemotherapy or induction and/or consolidation chemotherapy for AML.
  - Recommended starting dose is 5 mcg/kg/day subcutaneous injection, short intravenous infusion (15 to 30 minutes), or continuous intravenous infusion. See Full Prescribing Information for recommended dosage adjustments and timing of administration. (2.1)
- Patients with cancer undergoing bone marrow transplantation.
  - 10 mcg/kg/day given as an intravenous infusion no longer than 24 hours. See Full Prescribing Information for recommended dosage adjustments and timing of administration. (2.2)
- Patients undergoing autologous peripheral blood progenitor cell collection and therapy.
  - 10 mcg/kg/day subcutaneous injection. (2.3)
  - Administer for at least 4 days before first leukapheresis procedure and continue until last leukapheresis. (2.3)
- Patients with congenital neutropenia.
  - Recommended starting dose is 6 mcg/kg subcutaneous injection twice daily. (2.4)
- Patients with cyclic or idiopathic neutropenia.
  - Recommended starting dose is 5 mcg/kg subcutaneous injection daily. (2.4)
- Direct administration of less than 0.3 mL (180 mcg) using NIVESTYM prefilled syringe is not recommended due to potential for dosing errors. (2.5)

3 DOSAGE FORMS AND STRENGTHS

Vial

- Injection: 300 mcg/mL in a single-dose vial (3)
- Injection: 480 mcg/1.6 mL (300 mcg/mL) in a single-dose vial (3)

Prefilled Syringe

- Injection: 300 mcg/0.5 mL in a single-dose prefilled syringe (3)
- Injection: 480 mcg/0.8 mL in a single-dose prefilled syringe (3)

4 CONTRAINDICATIONS

Patients with a history of serious allergic reactions to human granulocyte colony-stimulating factors such as filgrastim products or pegfilgrastim products. (4)

5 WARNINGS AND PRECAUTIONS

- Fatal splenic rupture: Evaluate patients who report left upper abdominal or shoulder pain for an enlarged spleen or splenic rupture. (5.1)
- Acute respiratory distress syndrome (ARDS): Evaluate patients who develop fever and lung infiltrates or respiratory distress for ARDS.
- Discontinue NIVESTYM in patients with ARDS. (5.2)
- Serious allergic reactions, including anaphylaxis: Permanently discontinue NIVESTYM in patients with serious allergic reactions. (5.3)
- Fatal sickle cell crises: Discontinue NIVESTYM if sickle cell crisis occurs. (5.4)
- Glomerulonephritis: Evaluate and consider dose-reduction or interruption of NIVESTYM if causality is likely. (5.5)
- Myelodysplastic Syndrome (MDS) and Acute Myeloid Leukemia (AML): Monitor patients with breast and lung cancer using NIVESTYM in conjunction with chemotherapy and/or radiotherapy for signs and symptoms of MDS/AML. (5.8)
- Thrombocytopenia: Monitor platelet counts. (5.9)
- Aortitis: Aortitis has been reported in patients receiving NIVESTYM. Discontinue NIVESTYM if aortitis is suspected. (5.15)

6 ADVERSE REACTIONS

Most common adverse reactions in patients:

- With nonmyeloid malignancies receiving myelosuppressive anti-cancer drugs (≥ 5% difference in incidence compared to placebo) are pyrexia, pain, rash, cough, and dyspnea. (6.1)
- With AML (≥ 2% difference in incidence) are pain, epistaxis and rash. (6.1)
- With nonmyeloid malignancies undergoing myeloablative chemotherapy followed by BMT (≥ 5% difference in incidence) is rash. (6.1)
- Undergoing peripheral blood progenitor cell mobilization and collection (≥ 5% incidence) are bone pain, pyrexia and headache. (6.1)
- With severe chronic neutropenia (SCN) (≥ 5% difference in incidence) are pain, anemia, epistaxis, diarrhea, hypoesthesia and alopecia. (6.1)

To report SUSPECTED ADVERSE REACTIONS, contact Pfizer Inc at 1-800-438-1985 or FDA at 1-800-FDA-1088 or www.fda.gov/medwatch.

FULL PRESCRIBING INFORMATION

1 INDICATIONS AND USAGE

1.1 Patients with Cancer Receiving Myelosuppressive Chemotherapy

NIVESTYM is indicated to decrease the incidence of infection‚ as manifested by febrile neutropenia‚ in patients with nonmyeloid malignancies receiving myelosuppressive anti-cancer drugs associated with a significant incidence of severe neutropenia with fever [see Clinical Studies (14.1)].

1.2 Patients with Acute Myeloid Leukemia Receiving Induction or Consolidation Chemotherapy

NIVESTYM is indicated for reducing the time to neutrophil recovery and the duration of fever, following induction or consolidation chemotherapy treatment of patients with acute myeloid leukemia (AML) [see Clinical Studies (14.2)].

1.3 Patients with Cancer Undergoing Bone Marrow Transplantation

NIVESTYM is indicated to reduce the duration of neutropenia and neutropenia-related clinical sequelae‚ e.g.‚ febrile neutropenia, in patients with nonmyeloid malignancies undergoing myeloablative chemotherapy followed by bone marrow transplantation [see Clinical Studies (14.3)].

1.4 Patients Undergoing Autologous Peripheral Blood Progenitor Cell Collection and Therapy

NIVESTYM is indicated for the mobilization of autologous hematopoietic progenitor cells into the peripheral blood for collection by leukapheresis [see Clinical Studies (14.4)].

1.5 Patients with Severe Chronic Neutropenia

NIVESTYM is indicated for chronic administration to reduce the incidence and duration of sequelae of neutropenia (e.g.‚ fever‚ infections‚ oropharyngeal ulcers) in symptomatic patients with congenital neutropenia‚ cyclic neutropenia‚ or idiopathic neutropenia [see Clinical Studies (14.5)].

2 DOSAGE AND ADMINISTRATION

2.1 Dosage in Patients with Cancer Receiving Myelosuppressive Chemotherapy or Induction and/or Consolidation Chemotherapy for AML

The recommended starting dosage of NIVESTYM is 5 mcg/kg/day‚ administered as a single daily injection by subcutaneous injection‚ by short intravenous infusion (15 to 30 minutes)‚ or by continuous intravenous infusion. Obtain a complete blood count (CBC) and platelet count before instituting NIVESTYM therapy and monitor twice weekly during therapy. Consider dose escalation in increments of 5 mcg/kg for each chemotherapy cycle‚ according to the duration and severity of the absolute neutrophil count (ANC) nadir. Recommend stopping NIVESTYM if the ANC increases beyond 10‚000/mm^3 [see Warnings and Precautions (5.10)].

Administer NIVESTYM at least 24 hours after cytotoxic chemotherapy. Do not administer NIVESTYM within the 24-hour period prior to chemotherapy [see Warnings and Precautions (5.13)]. A transient increase in neutrophil count is typically seen 1 to 2 days after initiation of NIVESTYM therapy. Therefore, to ensure a sustained therapeutic response‚ administer NIVESTYM daily for up to 2 weeks or until the ANC has reached 10‚000/mm^3 following the expected chemotherapy-induced neutrophil nadir. The duration of NIVESTYM therapy needed to attenuate chemotherapy-induced neutropenia may be dependent on the myelosuppressive potential of the chemotherapy regimen employed.

2.2 Dosage in Patients with Cancer Undergoing Bone Marrow Transplantation

The recommended dosage of NIVESTYM following bone marrow transplantation (BMT) is 10 mcg/kg/day given as an intravenous infusion no longer than 24 hours. Administer the first dose of NIVESTYM at least 24 hours after cytotoxic chemotherapy and at least 24 hours after bone marrow infusion. Monitor CBCs and platelet counts frequently following marrow transplantation.

During the period of neutrophil recovery‚ titrate the daily dosage of NIVESTYM against the neutrophil response (see Table 1).

Table 1. Recommended Dosage Adjustments During Neutrophil Recovery in Patients with Cancer Following BMT
Absolute Neutrophil Count | NIVESTYM Dosage Adjustment
When ANC greater than 1,000/mm^3 for 3 consecutive days | Reduce to 5 mcg/kg/day [If ANC decreases to less than 1,000/mm^3 at any time during the 5 mcg/kg/day administration‚ increase NIVESTYM to 10 mcg/kg/day‚ and then follow the above steps.]
Then, if ANC remains greater than 1,000/mm^3 for 3 more consecutive days | Discontinue NIVESTYM
Then, if ANC decreases to less than 1,000/mm^3 | Resume at 5 mcg/kg/day

2.3 Dosage in Patients Undergoing Autologous Peripheral Blood Progenitor Cell Collection and Therapy

The recommended dosage of NIVESTYM for the mobilization of autologous peripheral blood progenitor cells (PBPC) is 10 mcg/kg/day given by subcutaneous injection. Administer NIVESTYM for at least 4 days before the first leukapheresis procedure and continue until the last leukapheresis. Although the optimal duration of NIVESTYM administration and leukapheresis schedule have not been established‚ administration of filgrastim for 6 to 7 days with leukaphereses on days 5‚ 6‚ and 7 was found to be safe and effective [see Clinical Studies (14.4)]. Monitor neutrophil counts after 4 days of NIVESTYM‚ and discontinue NIVESTYM if the white blood cell (WBC) count rises to greater than 100‚000/mm^3.

2.4 Dosage in Patients with Severe Chronic Neutropenia

Prior to starting NIVESTYM in patients with suspected chronic neutropenia, confirm the diagnosis of severe chronic neutropenia (SCN) by evaluating serial CBCs with differential and platelet counts‚ and evaluating bone marrow morphology and karyotype. The use of NIVESTYM prior to confirmation of a correct diagnosis of SCN may impair diagnostic efforts and may thus impair or delay evaluation and treatment of an underlying condition‚ other than SCN‚ causing the neutropenia.

The recommended starting dosage in patients with Congenital Neutropenia is 6 mcg/kg as a twice daily subcutaneous injection and the recommended starting dosage in patients with Idiopathic or Cyclic Neutropenia is 5 mcg/kg as a single daily subcutaneous injection.

Dosage Adjustments in Patients with Severe Chronic Neutropenia

Chronic daily administration is required to maintain clinical benefit. Individualize the dosage based on the patient's clinical course as well as ANC. In the SCN postmarketing surveillance study, the reported median daily doses of filgrastim were: 6 mcg/kg (congenital neutropenia), 2.1 mcg/kg (cyclic neutropenia), and 1.2 mcg/kg (idiopathic neutropenia). In rare instances, patients with congenital neutropenia have required doses of filgrastim greater than or equal to 100 mcg/kg/day.

Monitor CBCs for Dosage Adjustments

During the initial 4 weeks of NIVESTYM therapy and during the 2 weeks following any dosage adjustment‚ monitor CBCs with differential and platelet counts. Once a patient is clinically stable‚ monitor CBCs with differential and platelet counts monthly during the first year of treatment. Thereafter, if the patient is clinically stable, less frequent routine monitoring is recommended.

2.5 Important Administration Instructions

Patient self-administration and administration by a caregiver may benefit from training by a healthcare professional. Training should aim to demonstrate to those patients and caregivers how to measure the dose using the prefilled syringe, and the focus should be on ensuring that a patient or caregiver can successfully perform all of the steps in the Instructions for Use of NIVESTYM prefilled syringe with BD UltraSafe Plus™ Passive Needle Guard. If a patient or caregiver is not able to demonstrate that they can measure the dose and administer the product successfully, you should consider whether the patient is an appropriate candidate for self-administration of NIVESTYM [see Instructions for Use].

NIVESTYM prefilled syringe with BD UltraSafe Plus™ Passive Needle Guard is not designed to allow for direct administration of doses of less than 0.3 mL (180 mcg). The spring-mechanism of the needle guard apparatus affixed to the prefilled syringe interferes with the visibility of the graduation markings on the syringe barrel corresponding to 0.1 mL and 0.2 mL. The visibility of these markings is necessary to accurately measure doses of NIVESTYM less than 0.3 mL (180 mcg) for direct administration. Thus, the direct administration to patients requiring doses of less than 0.3 mL (180 mcg) is not recommended due to the potential for dosing errors. For direct administration of doses less than 0.3 mL (180 mcg) use NIVESTYM single-dose vial.

NIVESTYM is supplied in single-dose vials (for subcutaneous use or intravenous infusion) and single-dose prefilled syringes (for subcutaneous use) [see Dosage Forms and Strengths (3)]. Prior to use‚ remove the vial or prefilled syringe from the refrigerator and allow NIVESTYM to reach room temperature for a minimum of 30 minutes. If not used immediately, the vial or prefilled syringe may be stored at room temperature [between 20°C to 25°C (68°F to 77°F)] for up to 24 hours. Discard any vial or prefilled syringe left at room temperature for greater than 24 hours. Parenteral drug products should be inspected visually for particulate matter and discoloration prior to administration, whenever solution and container permit (the solution is clear and colorless). Do not administer NIVESTYM if particulates or discoloration are observed.

Discard unused portion of NIVESTYM in vials or prefilled syringes; do not re-enter the vial. Do not save unused drug for later administration.

Subcutaneous Injection

Inject NIVESTYM subcutaneously in the outer area of upper arms, abdomen, thighs, or upper outer areas of the buttock. If patients or caregivers are to administer NIVESTYM, instruct them in appropriate injection technique and ask them to follow the subcutaneous injection procedures in the Instructions for Use for the vial or prefilled syringe [see Patient Counseling Information (17)].

Training by the healthcare provider should aim to demonstrate to those patients and caregivers how to measure the dose of NIVESTYM, and the focus should be on ensuring that a patient or caregiver can successfully perform all of the steps in the Instructions for Use for the vial or prefilled syringe. If a patient or caregiver is not able to demonstrate that they can measure the dose and administer the product successfully, you should consider whether the patient is an appropriate candidate for self-administration of NIVESTYM or whether the patient would benefit from a different NIVESTYM presentation. If a patient or caregiver experiences difficulty measuring the required dose, especially if it is other than the entire contents of the NIVESTYM prefilled syringe, use of the NIVESTYM vial may be considered.

If the patient or caregiver misses a dose of NIVESTYM, instruct them to contact their healthcare provider.

Administration Instructions for the Prefilled Syringe

The NIVESTYM syringe plunger stopper and needle cover are not made with natural rubber latex.

Administration Instructions for Dilution (Vial Only)

If required for intravenous administration‚ NIVESTYM (vial only) may be diluted in 5% Dextrose Injection, USP from a concentration of 300 mcg/mL to 5 mcg/mL (do not dilute to a final concentration less than 5 mcg/mL). NIVESTYM diluted to concentrations from 5 mcg/mL to 15 mcg/mL should be protected from adsorption to plastic materials by the addition of Albumin (Human) to a final concentration of 2 mg/mL. When diluted in 5% Dextrose Injection, USP or 5% Dextrose plus Albumin (Human)‚ NIVESTYM is compatible with glass bottles‚ polyvinyl chloride (PVC) and polyolefin intravenous bags‚ and polypropylene syringes. Do not dilute with saline at any time because the product may precipitate.

Diluted NIVESTYM solution can be stored at room temperature for up to 24 hours. This 24-hour time period includes the time during room temperature storage of the infusion solution and the duration of the infusion.

3 DOSAGE FORMS AND STRENGTHS

NIVESTYM is a clear, colorless solution available as:

Vial:

- Injection: 300 mcg/mL in a single-dose vial
- Injection: 480 mcg/1.6 mL (300 mcg/mL) in a single-dose vial

Prefilled Syringe:

- Injection: 300 mcg/0.5 mL in a single-dose prefilled syringe
- Injection: 480 mcg/0.8 mL in a single-dose prefilled syringe

4 CONTRAINDICATIONS

NIVESTYM is contraindicated in patients with a history of serious allergic reactions to human granulocyte colony-stimulating factors such as filgrastim products or pegfilgrastim products [see Warnings and Precautions (5.3)].

5 WARNINGS AND PRECAUTIONS

5.1 Splenic Rupture

Splenic rupture, including fatal cases, has been reported following the administration of filgrastim products. Evaluate patients who report left upper abdominal or shoulder pain for an enlarged spleen or splenic rupture.

5.2 Acute Respiratory Distress Syndrome

Acute respiratory distress syndrome (ARDS) has been reported in patients receiving filgrastim products. Evaluate patients who develop fever and lung infiltrates or respiratory distress for ARDS. Discontinue NIVESTYM in patients with ARDS.

5.3 Serious Allergic Reactions

Serious allergic reactions, including anaphylaxis, have been reported in patients receiving filgrastim products. The majority of reported events occurred upon initial exposure. Provide symptomatic treatment for allergic reactions. Allergic reactions, including anaphylaxis, in patients receiving filgrastim products can recur within days after the discontinuation of initial anti-allergic treatment. Permanently discontinue NIVESTYM in patients with serious allergic reactions. NIVESTYM is contraindicated in patients with a history of serious allergic reactions to human granulocyte colony-stimulating factors such as filgrastim products or pegfilgrastim products.

5.4 Sickle Cell Disorders

Severe and sometimes fatal sickle cell crises can occur in patients with sickle cell disorders receiving filgrastim products. Discontinue NIVESTYM if sickle cell crisis occurs.

5.5 Glomerulonephritis

Glomerulonephritis has occurred in patients receiving filgrastim products. The diagnoses were based upon azotemia, hematuria (microscopic and macroscopic), proteinuria, and renal biopsy. Generally, events of glomerulonephritis resolved after dose reduction or discontinuation of filgrastim products. If glomerulonephritis is suspected, evaluate for cause. If causality is likely, consider dose-reduction or interruption of NIVESTYM.

5.6 Alveolar Hemorrhage and Hemoptysis

Alveolar hemorrhage manifesting as pulmonary infiltrates and hemoptysis requiring hospitalization have been reported in healthy donors treated with filgrastim products undergoing peripheral blood progenitor cell (PBPC) collection mobilization. Hemoptysis resolved with discontinuation of filgrastim products. The use of NIVESTYM for PBPC mobilization in healthy donors is not an approved indication.

5.7 Capillary Leak Syndrome

Capillary leak syndrome (CLS) has been reported after G-CSF administration, including filgrastim products, and is characterized by hypotension, hypoalbuminemia, edema and hemoconcentration. Episodes vary in frequency, severity and may be life-threatening if treatment is delayed. Patients who develop symptoms of capillary leak syndrome should be closely monitored and receive standard symptomatic treatment, which may include a need for intensive care.

5.8 Myelodysplastic Syndrome (MDS) and Acute Myeloid Leukemia (AML)

Patients with Severe Chronic Neutropenia

Confirm the diagnosis of SCN before initiating NIVESTYM therapy.

MDS and AML have been reported to occur in the natural history of congenital neutropenia without cytokine therapy. Cytogenetic abnormalities, transformation to MDS, and AML have also been observed in patients treated with filgrastim products for SCN. Based on available data including a postmarketing surveillance study, the risk of developing MDS and AML appears to be confined to the subset of patients with congenital neutropenia. Abnormal cytogenetics and MDS have been associated with the eventual development of myeloid leukemia. The effect of filgrastim products on the development of abnormal cytogenetics and the effect of continued filgrastim products administration in patients with abnormal cytogenetics or MDS are unknown. Monitor patients for signs and symptoms of MDS/AML in these settings. If a patient with SCN develops abnormal cytogenetics or myelodysplasia‚ the risks and benefits of continuing NIVESTYM should be carefully considered.

Patients with Breast and Lung Cancer

MDS and AML have been associated with the use of filgrastim products in conjunction with chemotherapy and/or radiotherapy in patients with breast and lung cancer. Monitor patients for signs and symptoms of MDS/AML in these settings.

5.9 Thrombocytopenia

Thrombocytopenia has been reported in patients receiving filgrastim products. Monitor platelet counts.

5.10 Leukocytosis

Patients with Cancer Receiving Myelosuppressive Chemotherapy

White blood cell counts of 100‚000/mm^3 or greater were observed in approximately 2% of patients receiving filgrastim at dosages above 5 mcg/kg/day. In patients with cancer receiving NIVESTYM as an adjunct to myelosuppressive chemotherapy‚ to avoid the potential risks of excessive leukocytosis‚ it is recommended that NIVESTYM therapy be discontinued if the ANC surpasses 10‚000/mm^3 after the chemotherapy-induced ANC nadir has occurred. Monitor CBCs at least twice weekly during therapy. Dosages of NIVESTYM that increase the ANC beyond 10‚000/mm^3 may not result in any additional clinical benefit. In patients with cancer receiving myelosuppressive chemotherapy‚ discontinuation of filgrastim therapy usually resulted in a 50% decrease in circulating neutrophils within 1 to 2 days‚ with a return to pretreatment levels in 1 to 7 days.

Peripheral Blood Progenitor Cell Collection and Therapy

During the period of administration of NIVESTYM for PBPC mobilization in patients with cancer, discontinue NIVESTYM if the leukocyte count rises to > 100,000/mm^3.

5.11 Cutaneous Vasculitis

Cutaneous vasculitis has been reported in patients treated with filgrastim products. In most cases‚ the severity of cutaneous vasculitis was moderate or severe. Most of the reports involved patients with SCN receiving long-term filgrastim therapy. Hold NIVESTYM therapy in patients with cutaneous vasculitis. NIVESTYM may be started at a reduced dose when the symptoms resolve and the ANC has decreased.

5.12 Potential Effect on Malignant Cells

NIVESTYM is a growth factor that primarily stimulates neutrophils. The granulocyte colony-stimulating factor (G-CSF) receptor through which NIVESTYM acts has also been found on tumor cell lines. The possibility that NIVESTYM acts as a growth factor for any tumor type cannot be excluded. The safety of filgrastim products in chronic myeloid leukemia (CML) and myelodysplasia has not been established.

When NIVESTYM is used to mobilize PBPC‚ tumor cells may be released from the marrow and subsequently collected in the leukapheresis product. The effect of reinfusion of tumor cells has not been well studied‚ and the limited data available are inconclusive.

5.13 Simultaneous Use with Chemotherapy and Radiation Therapy Not Recommended

The safety and efficacy of NIVESTYM given simultaneously with cytotoxic chemotherapy have not been established. Because of the potential sensitivity of rapidly dividing myeloid cells to cytotoxic chemotherapy‚ do not use NIVESTYM in the period 24 hours before through 24 hours after the administration of cytotoxic chemotherapy [see Dosage and Administration (2.2)].

The safety and efficacy of NIVESTYM have not been evaluated in patients receiving concurrent radiation therapy. Avoid the simultaneous use of NIVESTYM with chemotherapy and radiation therapy.

5.14 Nuclear Imaging

Increased hematopoietic activity of the bone marrow in response to growth factor therapy has been associated with transient positive bone-imaging changes. This should be considered when interpreting bone-imaging results.

5.15 Aortitis

Aortitis has been reported in patients receiving Filgrastim products. It may occur as early as the first week after start of therapy. Manifestations may include generalized signs and symptoms such as fever, abdominal pain, malaise, back pain, and increased inflammatory markers (e.g., c-reactive protein and white blood cell count). Consider aortitis in patients who develop these signs and symptoms without known etiology. Discontinue NIVESTYM if aortitis is suspected.

6 ADVERSE REACTIONS

The following serious adverse reactions are discussed in greater detail in other sections of the labeling:

- Splenic Rupture [see Warnings and Precautions (5.1)]
- Acute Respiratory Distress Syndrome [see Warnings and Precautions (5.2)]
- Serious Allergic Reactions [see Warnings and Precautions (5.3)]
- Sickle Cell Disorders [see Warnings and Precautions (5.4)]
- Glomerulonephritis [see Warnings and Precautions (5.5)]
- Alveolar Hemorrhage and Hemoptysis [see Warnings and Precautions (5.6)]
- Capillary Leak Syndrome [see Warnings and Precautions (5.7)]
- Myelodysplastic Syndrome [see Warnings and Precautions (5.8)]
- Acute Myeloid Leukemia [see Warnings and Precautions (5.8)]
- Thrombocytopenia [see Warnings and Precautions (5.9)]
- Leukocytosis [see Warnings and Precautions (5.10)]
- Cutaneous Vasculitis [see Warnings and Precautions (5.11)]
- Aortitis [see Warnings and Precautions (5.15)]

6.1 Clinical Trials Experience

Because clinical trials are conducted under widely varying conditions, adverse reaction rates observed in the clinical trials of a drug cannot be directly compared with rates in the clinical trials of another drug and may not reflect the rates observed in clinical practice.

Adverse Reactions in Patients with Cancer Receiving Myelosuppressive Chemotherapy

The following adverse reaction data in Table 2 are from three randomized, placebo-controlled studies in patients with:

- small cell lung cancer receiving standard dose chemotherapy with cyclophosphamide‚ doxorubicin‚ and etoposide (Study 1)
- small cell lung cancer receiving ifosfamide, doxorubicin‚ and etoposide (Study 2), and
- non-Hodgkin's lymphoma (NHL) receiving doxorubicin, cyclophosphamide, vindesine, bleomycin, methylprednisolone, and methotrexate ("ACVBP") or mitoxantrone, ifosfamide, mitoguazone, teniposide, methotrexate, folinic acid, methylprednisolone, and methotrexate ("VIM3") (Study 3).

A total of 451 patients were randomized to receive subcutaneous filgrastim 230 mcg/m^2 (Study 1), 240 mcg/m^2 (Study 2) or 4 or 5 mcg/kg/day (Study 3) (n = 294) or placebo (n = 157). The patients in these studies were median age 61 (range 29 to 78) years and 64% were male. The ethnicity was 95% Caucasian, 4% African American, and 1% Asian.

Table 2. Adverse Reactions in Patients with Cancer Receiving Myelosuppressive Chemotherapy (With ≥ 5% Higher Incidence in Filgrastim Compared to Placebo)
System Organ Class Preferred Term | Filgrastim (N = 294) | Placebo (N = 157)
Blood and lymphatic system disorders
Thrombocytopenia | 38% | 29%
Gastrointestinal disorders
Nausea | 43% | 32%
General disorders and administration site conditions
Pyrexia | 48% | 29%
Chest pain | 13% | 6%
Pain | 12% | 6%
Fatigue | 20% | 10%
Musculoskeletal and connective tissue disorders
Back pain | 15% | 8%
Arthralgia | 9% | 2%
Bone pain | 11% | 6%
Pain in extremity [Percent difference (Filgrastim – Placebo) was 4%.] | 7% | 3%
Nervous system disorders
Dizziness | 14% | 3%
Respiratory, thoracic and mediastinal disorders
Cough | 14% | 8%
Dyspnea | 13% | 8%
Skin and subcutaneous tissue disorders
Rash | 14% | 5%
Investigations
Blood lactate dehydrogenase increased | 6% | 1%
Blood alkaline phosphatase increased | 6% | 1%

Adverse events with ≥ 5% higher incidence in filgrastim patients compared to placebo and associated with the sequelae of the underlying malignancy or cytotoxic chemotherapy delivered included anemia, constipation, diarrhea, oral pain, vomiting, asthenia, malaise, edema peripheral, hemoglobin decreased, decreased appetite, oropharyngeal pain, and alopecia.

Adverse Reactions in Patients with Acute Myeloid Leukemia

Adverse reaction data below are from a randomized, double-blind, placebo-controlled study in patients with AML (Study 4) who received an induction chemotherapy regimen of intravenous daunorubicin days 1, 2, and 3; cytosine arabinoside days 1 to 7; and etoposide days 1 to 5 and up to 3 additional courses of therapy (induction 2, and consolidation 1, 2) of intravenous daunorubicin, cytosine arabinoside, and etoposide. The safety population included 518 patients randomized to receive either 5 mcg/kg/day filgrastim (n = 257) or placebo (n = 261). The median age was 54 (range 16 to 89) years and 54% were male.

Adverse reactions with ≥ 2% higher incidence in filgrastim patients compared to placebo included epistaxis, back pain, pain in extremity, erythema, and rash maculo-papular.

Adverse events with ≥ 2% higher incidence in filgrastim patients compared to placebo and associated with the sequelae of the underlying malignancy or cytotoxic chemotherapy included diarrhea, constipation, and transfusion reaction.

Adverse Reactions in Patients with Cancer Undergoing Bone Marrow Transplantation

The following adverse reaction data are from one randomized, no treatment-controlled study in patients with acute lymphoblastic leukemia or lymphoblastic lymphoma receiving high-dose chemotherapy (cyclophosphamide or cytarabine, and melphalan) and total body irradiation (Study 5) and one randomized, no treatment-controlled study in patients with Hodgkin's disease (HD) and NHL undergoing high-dose chemotherapy and autologous bone marrow transplantation (Study 6). Patients receiving autologous bone marrow transplantation only were included in the analysis. A total of 100 patients received either 30 mcg/kg/day as a 4-hour infusion (Study 5) or 10 mcg/kg/day or 30 mcg/kg/day as a 24-hour infusion (Study 6) filgrastim (n = 72), no treatment control or placebo (n = 28). The median age was 30 (range 15 to 57) years, 57% were male.

Adverse reactions with ≥ 5% higher incidence in filgrastim patients compared to patients receiving no filgrastim included rash and hypersensitivity.

Adverse reactions in patients receiving intensive chemotherapy followed by autologous BMT with ≥ 5% higher incidence in filgrastim patients compared to patients receiving no filgrastim included thrombocytopenia, anemia, hypertension, sepsis, bronchitis, and insomnia.

Adverse Reactions in Patients with Cancer Undergoing Autologous Peripheral Blood Progenitor Cell Collection

The adverse reaction data in Table 3 are from a series of 7 trials in patients with cancer undergoing mobilization of autologous peripheral blood progenitor cells for collection by leukapheresis. Patients (n = 166) in all these trials underwent a similar mobilization/collection regimen: filgrastim was administered for 6 to 8 days‚ in most cases the apheresis procedure occurred on days 5‚ 6, and 7. The dosage of filgrastim ranged between 5 to 30 mcg/kg/day and was administered subcutaneously by injection or continuous infusion. The median age was 39 (range 15 to 67) years, and 48% were male.

Table 3. Adverse Reactions in Patients with Cancer Undergoing Autologous PBPC in the Mobilization Phase (≥ 5% Incidence in Filgrastim Patients)
System Organ Class Preferred Term | Mobilization Phase (N = 166)
Musculoskeletal and connective tissue disorders
Bone pain | 30%
General disorders and administration site conditions
Pyrexia | 16%
Investigations
Blood alkaline phosphatase increased | 11%
Nervous system disorders
Headache | 10%

Adverse Reactions in Patients with Severe Chronic Neutropenia

The following adverse reaction data were identified in a randomized, controlled study in patients with SCN receiving filgrastim (Study 7). 123 patients were randomized to a 4-month observation period followed by subcutaneous filgrastim treatment or immediate subcutaneous filgrastim treatment. The median age was 12 years (range 7 months to 76 years) and 46% were male. The dosage of filgrastim was determined by the category of neutropenia. Initial dosage of filgrastim:

- Idiopathic neutropenia: 3.6 mcg/kg/day
- Cyclic neutropenia: 6 mcg/kg/day
- Congenital neutropenia: 6 mcg/kg/day divided 2 times per day

The dosage was increased incrementally to 12 mcg/kg/day divided 2 times per day if there was no response.

Adverse reactions with ≥ 5% higher incidence in filgrastim patients compared to patients receiving no filgrastim included arthralgia, bone pain, back pain, muscle spasms, musculoskeletal pain, pain in extremity, splenomegaly, anemia, upper respiratory tract infection, and urinary tract infection (upper respiratory tract infection and urinary tract infection were higher in the filgrastim arm, total infection related events were lower in filgrastim-treated patients), epistaxis, chest pain, diarrhea, hypoesthesia, and alopecia.

6.2 Postmarketing Experience

The following adverse reactions have been identified during post-approval use of filgrastim products. Because these reactions are reported voluntarily from a population of uncertain size, it is not always possible to reliably estimate their frequency or establish a causal relationship to drug exposure.

- splenic rupture and splenomegaly (enlarged spleen) [see Warnings and Precautions (5.1)]
- acute respiratory distress syndrome [see Warnings and Precautions (5.2)]
- anaphylaxis [see Warnings and Precautions (5.3)]
- sickle cell disorders [see Warnings and Precautions (5.4)]
- glomerulonephritis [see Warnings and Precautions (5.5)]
- alveolar hemorrhage and hemoptysis [see Warnings and Precautions (5.6)]
- capillary leak syndrome [see Warnings and Precautions (5.7)]
- leukocytosis [see Warnings and Precautions (5.10)]
- cutaneous vasculitis [see Warnings and Precautions (5.11)]
- Sweet's syndrome (acute febrile neutrophilic dermatosis)
- decreased bone density and osteoporosis in pediatric patients receiving chronic treatment with filgrastim products.
- myelodysplastic syndrome (MDS) and acute myeloid leukemia (AML) in patients with breast and lung cancer receiving chemotherapy and/or radiotherapy [see Warnings and Precautions (5.8)]
- aortitis [see Warnings and Precautions (5.15)]
- extramedullary hematopoiesis

8 USE IN SPECIFIC POPULATIONS

8.1 Pregnancy

Risk Summary

Available data from published studies, including several observational studies of pregnancy outcomes in women exposed to filgrastim products and those who were unexposed, have not established an association with filgrastim products use during pregnancy and major birth defects, miscarriage, or adverse maternal or fetal outcomes (see Data). Reports in the scientific literature have described transplacental passage of filgrastim in pregnant women when administered ≤ 30 hours prior to preterm delivery (≤ 30 weeks gestation). In animal reproduction studies, effects of filgrastim on prenatal development have been studied in rats and rabbits. No malformations were observed in either species. No maternal or fetal effects were observed in pregnant rats at doses up to 58 times the human doses. Filgrastim has been shown to have adverse effects in pregnant rabbits at doses 2 to 10 times higher than the human doses (see Data).

The estimated background risk of major birth defects and miscarriage for the indicated populations is unknown. All pregnancies have a background risk of birth defect, loss, or other adverse outcomes. In the U.S. general population, the estimated background risks of major birth defects and miscarriage in clinically recognized pregnancies is 2–4% and 15–20%, respectively.

Data

Human data

Several observational studies based on the Severe Chronic Neutropenia International Registry (SCNIR) described pregnancy outcomes in women with severe chronic neutropenia (SCN) who were exposed to filgrastim products during pregnancy and women with SCN who were unexposed. No major differences were seen between treated and untreated women with respect to pregnancy outcome (including miscarriage and preterm labor), newborn complications (including birth weight) and infections. Methodological limitations of these studies, include small sample size, and lack of generalizability due to the underlying maternal condition.

Animal data

Effects of filgrastim on prenatal development have been studied in rats and rabbits. No malformations were observed in either species. Filgrastim has been shown to have adverse effects in pregnant rabbits at doses 2 to 10 times higher than the human doses. In pregnant rabbits showing signs of maternal toxicity, reduced embryo-fetal survival (at 20 and 80 mcg/kg/day) and increased abortions (at 80 mcg/kg/day) were observed. In pregnant rats, no maternal or fetal effects were observed at doses up to 575 mcg/kg/day, which is approximately 58 times higher than the human dose of 10 mcg/kg/day.

Offspring of rats administered filgrastim during the peri-natal and lactation periods exhibited a delay in external differentiation and growth retardation (≥ 20 mcg/kg/day) and slightly reduced survival rate (100 mcg/kg/day).

8.2 Lactation

Risk Summary

There is published literature documenting transfer of filgrastim into human milk. There are a few case reports describing the use of filgrastim in breastfeeding mothers with no adverse effects noted in the infants. There are no data on the effects of filgrastim products on milk production. Other filgrastim products are secreted poorly into breast milk, and filgrastim products are not absorbed orally by neonates. The developmental and health benefits of breastfeeding should be considered along with the mother's clinical need for NIVESTYM and any potential adverse effects on the breastfed child from NIVESTYM or from the underlying maternal condition.

8.4 Pediatric Use

NIVESTYM prefilled syringe with BD UltraSafe Plus™ Passive Needle Guard may not accurately measure volumes less than 0.3 mL due to the needle spring mechanism design. Therefore, the direct administration of a volume less than 0.3 mL using NIVESTYM prefilled syringe is not recommended due to the potential for dosing errors. For direct administration of doses less than 0.3 mL (180 mcg) use NIVESTYM single-dose vial.

In patients with cancer receiving myelosuppressive chemotherapy‚ 15 pediatric patients median age 2.6 (range 1.2 to 9.4) years with neuroblastoma were treated with myelosuppressive chemotherapy (cyclophosphamide‚ cisplatin‚ doxorubicin‚ and etoposide) followed by subcutaneous filgrastim at doses of 5, 10, or 15 mcg/kg/day for 10 days (n = 5/dose) (Study 8). The pharmacokinetics of filgrastim in pediatric patients after chemotherapy were similar to those in adults receiving the same weight-normalized doses, suggesting no age-related differences in the pharmacokinetics of filgrastim. In this population‚ filgrastim was well-tolerated. There was one report of palpable splenomegaly and one report of hepatosplenomegaly associated with filgrastim therapy; however‚ the only consistently reported adverse event was musculoskeletal pain‚ which is no different from the experience in the adult population.

The safety and effectiveness of NIVESTYM have been established in pediatric patients with SCN [see Clinical Studies (14.5)]. Use of NIVESTYM for this indication is supported by NIVESTYM’s approval as a biosimilar to filgrastim and evidence from a phase 3 study (Study 7) to assess the safety and efficacy of filgrastim in the treatment of SCN where 123 patients with a median age of 12 years (range 7 months to 76 years) were studied. Of the 123 patients, 12 were infants (7 months to 2 years of age), 49 were children (2 to 12 years of age), and 9 were adolescents (12 to 16 years of age). Additional information is available from a SCN postmarketing surveillance study, which includes long-term follow-up of patients in the clinical studies and information from additional patients who entered directly into the postmarketing surveillance study. Of the 731 patients in the surveillance study, 429 were pediatric patients < 18 years of age (range 0.9 to 17) [see Indications and Usage (1.5), Dosage and Administration (2.5), and Clinical Studies (14.5)].

Long-term follow-up data from the postmarketing surveillance study suggest that height and weight are not adversely affected in patients who received up to 5 years of filgrastim treatment. Limited data from patients who were followed in the phase 3 study for 1.5 years did not suggest alterations in sexual maturation or endocrine function.

Pediatric patients with congenital types of neutropenia (Kostmann's syndrome, congenital agranulocytosis, or Schwachman-Diamond syndrome) have developed cytogenetic abnormalities and have undergone transformation to MDS and AML while receiving chronic filgrastim treatment. The relationship of these events to filgrastim product administration is unknown [see Warnings and Precautions (5.8) and Adverse Reactions (6)].

8.5 Geriatric Use

Among 855 subjects enrolled in 3 randomized, placebo-controlled trials of filgrastim-treated patients receiving myelosuppressive chemotherapy, there were 232 subjects age 65 or older, and 22 subjects age 75 or older. No overall differences in safety or effectiveness were observed between these subjects and younger subjects.

Clinical studies of filgrastim in other approved indications (i.e., BMT recipients, PBPC mobilization, and SCN) did not include sufficient numbers of subjects aged 65 and older to determine whether elderly subjects respond differently from younger subjects.

10 OVERDOSAGE

The maximum tolerated dose of filgrastim products has not been determined. In filgrastim clinical trials of patients with cancer receiving myelosuppressive chemotherapy‚ WBC counts > 100‚000/mm^3 have been reported in less than 5% of patients‚ but were not associated with any reported adverse clinical effects. Patients in the BMT studies received up to 138 mcg/kg/day without toxic effects‚ although there was a flattening of the dose response curve above daily doses of greater than 10 mcg/kg/day.

11 DESCRIPTION

Filgrastim-aafi is a 175 amino acid human granulocyte colony-stimulating factor (G-CSF) manufactured by recombinant DNA technology. NIVESTYM is produced by Escherichia coli (E coli) bacteria into which has been inserted the human granulocyte colony-stimulating factor gene. NIVESTYM has a molecular weight of 18‚799 daltons. The protein has an amino acid sequence that is identical to the natural sequence predicted from human DNA sequence analysis‚ except for the addition of an N-terminal methionine necessary for expression in E coli. Because NIVESTYM is produced in E coli‚ the product is non-glycosylated and thus differs from G-CSF isolated from a human cell.

NIVESTYM is a sterile‚ clear‚ colorless‚ preservative-free liquid containing filgrastim-aafi injection for subcutaneous or intravenous use. The product is available in single-dose vials for subcutaneous or intravenous use and prefilled syringes for subcutaneous use. The single-dose vials contain either 300 mcg/mL or 480 mcg/1.6 mL of filgrastim-aafi. The single-dose prefilled syringes contain either 300 mcg/0.5 mL or 480 mcg/0.8 mL of filgrastim-aafi. The final pH range of the NIVESTYM drug product solution is 3.8 to 4.3. See Table 4 below for product composition of each single-dose vial or prefilled syringe.

Table 4. Product Composition
 | 300 mcg/mL Vial | 480 mcg/1.6 mL Vial | 300 mcg/0.5 mL Syringe | 480 mcg/0.8 mL Syringe
Filgrastim-aafi | 300 mcg | 480 mcg | 300 mcg | 480 mcg
Acetate | 0.59 mg | 0.94 mg | 0.295 mg | 0.472 mg
Polysorbate 80 | 0.04 mg | 0.064 mg | 0.02 mg | 0.032 mg
Sodium | 0.035 mg | 0.056 mg | 0.0175 mg | 0.028 mg
Sorbitol | 50 mg | 80 mg | 25 mg | 40 mg
Water for Injection USP q.s. ad [quantity sufficient to make] | 1 mL | 1.6 mL | 0.5 mL | 0.8 mL

12 CLINICAL PHARMACOLOGY

12.1 Mechanism of Action

Colony-stimulating factors are glycoproteins which act on hematopoietic cells by binding to specific cell surface receptors and stimulating proliferation‚ differentiation commitment‚ and some end-cell functional activation.

Endogenous G-CSF is a lineage-specific colony-stimulating factor that is produced by monocytes‚ fibroblasts, and endothelial cells. G-CSF regulates the production of neutrophils within the bone marrow and affects neutrophil progenitor proliferation‚ differentiation, and selected end-cell functions (including enhanced phagocytic ability‚ priming of the cellular metabolism associated with respiratory burst‚ antibody-dependent killing, and the increased expression of some cell surface antigens). G-CSF is not species-specific and has been shown to have minimal direct in vivo or in vitro effects on the production or activity of hematopoietic cell types other than the neutrophil lineage.

12.2 Pharmacodynamics

In phase 1 studies involving 96 patients with various non-myeloid malignancies‚ filgrastim administration resulted in a dose-dependent increase in circulating neutrophil counts over the dose range of 1 to 70 mcg/kg/day. This increase in neutrophil counts was observed whether filgrastim was administered intravenous (1 to 70 mcg/kg twice daily)‚ subcutaneous (1 to 3 mcg/kg once daily)‚ or by continuous subcutaneous infusion (3 to 11 mcg/kg/day). With discontinuation of filgrastim therapy‚ neutrophil counts returned to baseline in most cases within 4 days. Isolated neutrophils displayed normal phagocytic (measured by zymosan-stimulated chemoluminescence) and chemotactic (measured by migration under agarose using N-formyl-methionyl-leucyl-phenylalanine [fMLP] as the chemotaxin) activity in vitro.

The absolute monocyte count was reported to increase in a dose-dependent manner in most patients receiving filgrastim; however‚ the percentage of monocytes in the differential count remained within the normal range. Absolute counts of both eosinophils and basophils did not change and were within the normal range following administration of filgrastim. Increases in lymphocyte counts following filgrastim administration have been reported in some normal subjects and patients with cancer.

White blood cell (WBC) differentials obtained during clinical trials have demonstrated a shift towards earlier granulocyte progenitor cells (left shift)‚ including the appearance of promyelocytes and myeloblasts‚ usually during neutrophil recovery following the chemotherapy-induced nadir. In addition‚ Dohle bodies‚ increased granulocyte granulation‚ and hypersegmented neutrophils have been observed. Such changes were transient and were not associated with clinical sequelae, nor were they necessarily associated with infection.

12.3 Pharmacokinetics

Filgrastim products exhibit nonlinear pharmacokinetics. Clearance is dependent on filgrastim product concentration and neutrophil count: G-CSF receptor-mediated clearance is saturated by high concentration of filgrastim products and is diminished by neutropenia. In addition, filgrastim products are cleared by the kidney.

Subcutaneous administration of 3.45 mcg/kg and 11.5 mcg/kg of filgrastim resulted in maximum serum concentrations of 4 and 49 ng/mL‚ respectively‚ within 2 to 8 hours. After intravenous administration, the volume of distribution averaged 150 mL/kg and the elimination half-life was approximately 3.5 hours in both normal subjects and cancer subjects. Clearance rates of filgrastim were approximately 0.5 to 0.7 mL/minute/kg. Single parenteral doses or daily intravenous doses‚ over a 14-day period‚ resulted in comparable half-lives. The half-lives were similar for intravenous administration (231 minutes‚ following doses of 34.5 mcg/kg) and for subcutaneous administration (210 minutes‚ following filgrastim dosages of 3.45 mcg/kg). Continuous 24-hour intravenous infusions of 20 mcg/kg over an 11 to 20-day period produced steady-state serum concentrations of filgrastim with no evidence of drug accumulation over the time period investigated. The absolute bioavailability of filgrastim after subcutaneous administration is 60% to 70%.

Specific Populations

Pediatric Patients

The pharmacokinetics of filgrastim in pediatric patients after chemotherapy are similar to those in adult patients receiving the same weight-normalized doses, suggesting no age-related differences in the pharmacokinetics of filgrastim products [see Use in Specific Populations (8.4)].

Renal Impairment

In a study with healthy volunteers, subjects with moderate renal impairment, and subjects with end-stage renal disease (n = 4 per group), higher serum concentrations were observed in subjects with end-stage renal disease. However, dose adjustment in patients with renal impairment is not necessary.

Hepatic Impairment

Pharmacokinetics and pharmacodynamics of filgrastim are similar between subjects with hepatic impairment and healthy subjects (n = 12/group). The study included 10 subjects with mild hepatic impairment (Child-Pugh Class A) and 2 subjects with moderate hepatic impairment (Child-Pugh Class B). Therefore, NIVESTYM dose adjustment for patients with hepatic impairment is not necessary.

12.6 Immunogenicity

The observed incidence of anti-drug antibodies is highly dependent on the sensitivity and specificity of the assay. Differences in assay methods preclude meaningful comparisons of the incidence of anti-drug antibodies in the studies described below with the incidence of anti-drug antibodies in other studies, including those of filgrastim or of other filgrastim products.

While available data suggest that a small proportion of patients developed binding antibodies to filgrastim products, the nature and specificity of these antibodies has not been adequately studied. In clinical studies using filgrastim, the incidence of antibodies binding to filgrastim was 3% (11/333). In these 11 patients, no evidence of a neutralizing response was observed using a cell-based bioassay. Because of the low occurrence of anti-drug antibodies, the effect of these antibodies on the pharmacokinetics, pharmacodynamics, safety, and/or effectiveness of filgrastim products is unknown.

Cytopenias resulting from an antibody response to exogenous growth factors have been reported on rare occasions in patients treated with other recombinant growth factors.

13 NONCLINICAL TOXICOLOGY

13.1 Carcinogenesis, Mutagenesis, Impairment of Fertility

The carcinogenic potential of filgrastim products has not been studied. Filgrastim failed to induce bacterial gene mutations in either the presence or absence of a drug metabolizing enzyme system. Filgrastim had no observed effect on the fertility of male or female rats at doses up to 500 mcg/kg.

13.2 Animal Toxicology and Pharmacology

Filgrastim was administered to monkeys‚ dogs‚ hamsters‚ rats‚ and mice as part of a nonclinical toxicology program, which included studies up to 1 year duration. In the repeated-dose studies‚ changes observed were attributable to the expected pharmacological actions of filgrastim (i.e.‚ dose-dependent increases in white blood cell counts‚ increased circulating segmented neutrophils‚ and increased myeloid: erythroid ratio in bone marrow). Histopathologic examination of the liver and spleen revealed evidence of ongoing extramedullary granulopoiesis, and dose-related increases in spleen weight were seen in all species. These changes all reversed after discontinuation of treatment.

14 CLINICAL STUDIES

14.1 Patients with Cancer Receiving Myelosuppressive Chemotherapy

The safety and efficacy of filgrastim to decrease the incidence of infection‚ as manifested by febrile neutropenia‚ in patients with nonmyeloid malignancies receiving myelosuppressive anti-cancer drugs were established in a randomized‚ double-blind‚ placebo-controlled trial conducted in patients with small cell lung cancer (Study 1).

In Study 1, patients received up to 6 cycles of intravenous chemotherapy including intravenous cyclophosphamide and doxorubicin on day 1; and etoposide on days 1, 2, and 3 of 21 day cycles. Patients were randomized to receive filgrastim (n = 99) at a dose of 230 mcg/m^2 (4 to 8 mcg/kg/day) or placebo (n = 111). Study drug was administered subcutaneously daily beginning on day 4, for a maximum of 14 days. A total of 210 patients were evaluable for efficacy and 207 were evaluable for safety. The demographic and disease characteristics were balanced between arms with a median age of 62 (range 31 to 80) years; 64% males; 89% Caucasian; 72% extensive disease and 28% limited disease.

The main efficacy endpoint was the incidence of febrile neutropenia. Febrile neutropenia was defined as an ANC < 1,000/mm^3 and temperature > 38.2°C. Treatment with filgrastim resulted in a clinically and statistically significant reduction in the incidence of infection‚ as manifested by febrile neutropenia, 40% for filgrastim-treated patients and 76% for placebo-treated patients (p < 0.001). There were also statistically significant reductions in the incidence and overall duration of infection manifested by febrile neutropenia; the incidence, severity and duration of severe neutropenia (ANC < 500/mm^3); the incidence and overall duration of hospital admissions; and the number of reported days of antibiotic use.

14.2 Patients with Acute Myeloid Leukemia Receiving Induction or Consolidation Chemotherapy

The safety and efficacy of filgrastim to reduce the time to neutrophil recovery and the duration of fever, following induction or consolidation chemotherapy treatment of patients with acute myeloid leukemia (AML) was established in a randomized, double-blind‚ placebo-controlled‚ multi-center trial in patients with newly diagnosed, de novo AML (Study 4).

In Study 4 the initial induction therapy consisted of intravenous daunorubicin days 1, 2, and 3; cytosine arabinoside days 1 to 7; and etoposide days 1 to 5. Patients were randomized to receive subcutaneous filgrastim (n = 259) at a dose of 5 mcg/kg/day or placebo (n = 262) from 24 hours after the last dose of chemotherapy until neutrophil recovery (ANC ≥ 1,000/mm^3 for 3 consecutive days or ≥ 10,000/mm^3 for 1 day) or for a maximum of 35 days. The demographic and disease characteristics were balanced between arms with a median age of 54 (range 16 to 89) years; 54% males; initial white blood cell count (65% < 25,000/mm^3 and 27% > 100,000/mm^3); 29% unfavorable cytogenetics.

The main efficacy endpoint was median duration of severe neutropenia defined as neutrophil count < 500/mm^3. Treatment with filgrastim resulted in a clinically and statistically significant reduction in median number of days of severe neutropenia, filgrastim-treated patients 14 days, placebo-treated patients 19 days (p = 0.0001: difference of 5 days (95% CI: -6.0, -4.0)).

There was a reduction in the median duration of intravenous antibiotic use, filgrastim-treated patients: 15 days versus placebo-treated patients: 18.5 days; a reduction in the median duration of hospitalization, filgrastim-treated patients: 20 days versus placebo-treated patients: 25 days.

There were no statistically significant differences between the filgrastim and the placebo groups in complete remission rate (69% - filgrastim, 68% - placebo), median time to progression of all randomized patients (165 days - filgrastim, 186 days - placebo), or median overall survival (380 days - filgrastim, 425 days - placebo).

14.3 Patients with Cancer Undergoing Bone Marrow Transplantation

The safety and efficacy of filgrastim to reduce the duration of neutropenia in patients with nonmyeloid malignancies undergoing myeloablative chemotherapy followed by autologous bone marrow transplantation was evaluated in 2 randomized controlled trials of patients with lymphoma (Study 6 and Study 9). The safety and efficacy of filgrastim to reduce the duration of neutropenia in patients undergoing myeloablative chemotherapy followed by allogeneic bone marrow transplantation was evaluated in a randomized placebo-controlled trial (Study 10).

In Study 6 patients with Hodgkin's disease received a preparative regimen of intravenous cyclophosphamide, etoposide, and BCNU ("CVP"), and patients with non-Hodgkin's lymphoma received intravenous BCNU, etoposide, cytosine arabinoside and melphalan ("BEAM"). There were 54 patients randomized 1:1:1 to control, filgrastim 10 mcg/kg/day, and filgrastim 30 mcg/kg/day as a 24-hour continuous infusion starting 24 hours after bone marrow infusion for a maximum of 28 days. The median age was 33 (range 17 to 57) years; 56% males; 69% Hodgkin's disease and 31% non-Hodgkin's lymphoma.

The main efficacy endpoint was duration of severe neutropenia ANC < 500/mm^3. A statistically significant reduction in the median number of days of severe neutropenia (ANC < 500/mm^3) occurred in the filgrastim-treated groups versus the control group (23 days in the control group‚ 11 days in the 10 mcg/kg/day group, and 14 days in the 30 mcg/kg/day group [11 days in the combined treatment groups‚ p = 0.004]).

In Study 9, patients with Hodgkin's disease and non-Hodgkin's lymphoma received a preparative regimen of intravenous cyclophosphamide, etoposide, and BCNU ("CVP"). There were 43 evaluable patients randomized to continuous subcutaneous infusion filgrastim 10 mcg/kg/day (n = 19), filgrastim 30 mcg/kg/day (n = 10) and no treatment (n = 14) starting the day after marrow infusion for a maximum of 28 days. The median age was 33 (range 17 to 56) years; 67% males; 28% Hodgkin's disease and 72% non-Hodgkin's lymphoma.

The main efficacy endpoint was duration of severe neutropenia. There was statistically significant reduction in the median number of days of severe neutropenia (ANC < 500/mm^3) in the filgrastim-treated groups versus the control group (21.5 days in the control group versus 10 days in the filgrastim-treated groups, p < 0.001). The number of days of febrile neutropenia was also reduced significantly in this study (13.5 days in the control group versus 5 days in the filgrastim-treated groups‚ p < 0.0001).

In Study 10, 70 patients scheduled to undergo bone marrow transplantation for multiple underlying conditions using multiple preparative regimens were randomized to receive filgrastim 300 mcg/m^2/day (n = 33) or placebo (n = 37) days 5 through 28 after marrow infusion. The median age was 18 (range 1 to 45) years, 56% males. The underlying disease was: 67% hematologic malignancy, 24% aplastic anemia, 9% other. A statistically significant reduction in the median number of days of severe neutropenia occurred in the treated group versus the control group (19 days in the control group and 15 days in the treatment group‚ p < 0.001) and time to recovery of ANC to ≥ 500/mm^3 (21 days in the control group and 16 days in the treatment group‚ p < 0.001).

14.4 Patients Undergoing Autologous Peripheral Blood Progenitor Cell Collection and Therapy

The safety and efficacy of filgrastim to mobilize autologous peripheral blood progenitor cells for collection by leukapheresis was supported by the experience in uncontrolled trials, and a randomized trial comparing hematopoietic stem cell rescue using filgrastim mobilized autologous peripheral blood progenitor cells to autologous bone marrow (Study 11). Patients in all these trials underwent a similar mobilization/collection regimen: filgrastim was administered for 6 to 7 days‚ in most cases the apheresis procedure occurred on days 5‚ 6, and 7. The dose of filgrastim ranged between 10 to 24 mcg/kg/day and was administered subcutaneously by injection or continuous intravenous infusion.

Engraftment was evaluated in 64 patients who underwent transplantation using filgrastim mobilized autologous hematopoietic progenitor cells in uncontrolled trials. Two of the 64 patients (3%) did not achieve the criteria for engraftment as defined by a platelet count ≥ 20‚000/mm^3 by day 28. In clinical trials of filgrastim for the mobilization of hematopoietic progenitor cells‚ filgrastim was administered to patients at doses between 5 to 24 mcg/kg/day after reinfusion of the collected cells until a sustainable ANC (≥ 500/mm^3) was reached. The rate of engraftment of these cells in the absence of filgrastim post transplantation has not been studied.

Study 11 was a randomized, unblinded study of patients with Hodgkin's disease or non-Hodgkin's lymphoma undergoing myeloablative chemotherapy‚ 27 patients received filgrastim-mobilized autologous hematopoietic progenitor cells and 31 patients received autologous bone marrow. The preparative regimen was intravenous BCNU, etoposide, cytosine arabinoside and melphalan ("BEAM"). Patients received daily filgrastim 24 hours after stem cell infusion at a dose of 5 mcg/kg/day. The median age was 33 (range 1 to 59) years; 64% males; 57% Hodgkin's disease and 43% non-Hodgkin's lymphoma. The main efficacy endpoint was number of days of platelet transfusions. Patients randomized to filgrastim-mobilized autologous peripheral blood progenitor cells compared to autologous bone marrow had significantly fewer days of platelet transfusions (median 6 vs 10 days).

14.5 Patients with Severe Chronic Neutropenia

The safety and efficacy of filgrastim to reduce the incidence and duration of sequelae of neutropenia (that is fever‚ infections, oropharyngeal ulcers) in symptomatic adult and pediatric patients with congenital neutropenia‚ cyclic neutropenia‚ or idiopathic neutropenia was established in a randomized controlled trial conducted in patients with severe neutropenia (Study 7).

Patients eligible for Study 7 had a history of severe chronic neutropenia documented with an ANC < 500/mm^3 on three occasions during a 6-month period, or in patients with cyclic neutropenia 5 consecutive days of ANC < 500/mm^3 per cycle. In addition, patients must have experienced a clinically significant infection during the previous 12 months. Patients were randomized to a 4-month observation period followed by filgrastim treatment or immediate filgrastim treatment. The median age was 12 years (range 7 months to 76 years); 46% males; 34% idiopathic, 17% cyclic and 49% congenital neutropenia.

Filgrastim was administered subcutaneously. The dose of filgrastim was determined by the category of neutropenia. Initial dose of filgrastim:

- Idiopathic neutropenia: 3.6 mcg/kg/day
- Cyclic neutropenia: 6 mcg/kg/day
- Congenital neutropenia: 6 mcg/kg/day divided 2 times per day

The dose was increased incrementally to 12 mcg/kg/day divided 2 times per day if there was no response.

The main efficacy endpoint was response to filgrastim treatment. ANC response from baseline (< 500/mm^3) was defined as follows:

- Complete response: median ANC > 1,500/mm^3
- Partial response: median ANC ≥ 500/mm^3 and ≤ 1,500/mm^3 with a minimum increase of 100%
- No response: median ANC < 500/mm^3

There were 112 of 123 patients who demonstrated a complete or partial response to filgrastim treatment.

Additional efficacy endpoints included a comparison between patients randomized to 4 months of observation and patients receiving filgrastim of the following parameters:

- incidence of infection
- incidence of fever
- duration of fever
- incidence, duration, and severity of oropharyngeal ulcers
- number of days of antibiotic use

The incidence for each of these 5 clinical parameters was lower in the filgrastim arm compared to the control arm for cohorts in each of the 3 major diagnostic categories. An analysis of variance showed no significant interaction between treatment and diagnosis‚ suggesting that efficacy did not differ substantially in the different diseases. Although filgrastim substantially reduced neutropenia in all patient groups‚ in patients with cyclic neutropenia‚ cycling persisted but the period of neutropenia was shortened to 1 day.

16 HOW SUPPLIED/STORAGE AND HANDLING

NIVESTYM injection is a clear, colorless, preservative-free solution supplied as:

Vials

Single-dose vials containing 300 mcg/mL of filgrastim-aafi solution. Dispensing packs of 10 vials (NDC 0069-0293-10).

Single-dose vials containing 480 mcg/1.6 mL (300 mcg/mL) of filgrastim-aafi solution. Dispensing packs of 10 vials (NDC 0069-0294-10).

Prefilled Syringes

Single-dose prefilled syringe with BD UltraSafe Plus™ Passive Needle Guard, containing 300 mcg/0.5 mL of filgrastim-aafi solution.

- Pack of 1 prefilled syringe (NDC 0069-0291-01).
- Pack of 10 prefilled syringes (NDC 0069-0291-10).

Single-dose, prefilled syringe with BD UltraSafe Plus™ Passive Needle Guard, containing 480 mcg/0.8 mL of filgrastim-aafi solution.

- Pack of 1 prefilled syringe (NDC 0069-0292-01).
- Pack of 10 prefilled syringes (NDC 0069-0292-10).

The NIVESTYM syringe plunger stopper and needle cover are not made with natural rubber latex [see Dosage and Administration (2.5)].

Storage

Store NIVESTYM in the refrigerator at 2°C to 8°C (36°F to 46°F) in the original carton to protect from light. Do not leave NIVESTYM in direct sunlight. Avoid freezing; if frozen, thaw in the refrigerator before administration. Discard NIVESTYM if frozen more than once. Avoid shaking. Transport via a pneumatic tube has not been studied.

17 PATIENT COUNSELING INFORMATION

Advise the patient to read the FDA-approved patient labeling (Patient Information and Instructions for Use). Review the steps for direct patient administration with patients and caregivers. Training by the healthcare provider should aim to ensure that patients and caregivers can successfully perform all of the steps in the Instructions for Use of NIVESTYM vial and prefilled syringe, including showing the patient or caregiver how to measure the required dose, particularly if a patient is on a dose other than the entire prefilled syringe. If a patient or caregiver is not able to demonstrate that they can measure the dose and administer the product successfully, you should consider whether the patient is an appropriate candidate for self-administration of NIVESTYM or whether the patient would benefit from a different NIVESTYM presentation. Advise patients of the following risks and potential risks with NIVESTYM:

- Rupture or enlargement of the spleen may occur. Symptoms include left upper quadrant abdominal pain or left shoulder pain. Advise patients to report pain in these areas to their physician immediately [see Warnings and Precautions (5.1)].
- Dyspnea, with or without fever, progressing to Acute Respiratory Distress Syndrome, may occur.
  Advise patients to report dyspnea to their physician immediately [see Warnings and Precautions (5.2)].
- Serious allergic reactions may occur, which may be signaled by rash‚ facial edema‚ wheezing‚ dyspnea‚ hypotension‚ or tachycardia. Advise patients to seek immediate medical attention if signs or symptoms of hypersensitivity reaction occur [see Warnings and Precautions (5.3)].
- In patients with sickle cell disease, sickle cell crisis and death have occurred. Discuss potential risks and benefits for patients with sickle cell disease prior to the administration of human granulocyte colony-stimulating factors [see Warnings and Precautions (5.4)].
- Glomerulonephritis may occur. Symptoms include swelling of the face or ankles, dark colored urine or blood in the urine, or a decrease in urine production. Advise patients to report signs or symptoms of glomerulonephritis to their physician immediately [see Warnings and Precautions (5.5)].
- There may be an increased risk of Myelodysplastic Syndrome and/or Acute Myeloid Leukemia in patients with congenital neutropenia who receive filgrastim products and in patients with breast and lung cancer who receive filgrastim products in conjunction with chemotherapy and/or radiation therapy. Symptoms of MDS and AML may include tiredness, fever, and easy bruising or bleeding. Advise patients to report to their physician signs and symptoms of MDS/AML [see Warnings and Precautions (5.8)].
- Cutaneous vasculitis may occur, which may be signaled by purpura or erythema. Advise patients to report signs or symptoms of vasculitis to their physician immediately [see Warnings and Precautions (5.11)].
- Aortitis may occur. Symptoms may include fever, abdominal pain, malaise, back pain, and increased inflammatory markers. Advise patients to report signs and symptoms of aortitis to their physician immediately [see Warnings and Precautions (5.15)].

Instruct patients who self-administer NIVESTYM using the prefilled syringe or single-dose vial of the:

- Importance of following the applicable Instructions for Use.
- Dangers of reusing needles, syringes, or unused portions of single-dose vials.
- Importance of following local requirements for proper disposal of used syringes, needles, and unused vials.
- Importance of informing the healthcare provider if difficulty occurs when measuring or administering partial contents of the NIVESTYM prefilled syringe. If difficulty occurs, use of the NIVESTYM vial may be considered.
- Difference in product concentration of the NIVESTYM prefilled syringe in comparison to the NIVESTYM vial. When switching patients from the NIVESTYM prefilled syringe to the NIVESTYM vial, or vice versa, ensure that patients understand the correct volume to be administered since the concentration of NIVESTYM differs between the prefilled syringe and the vial.

This product's labeling may have been updated. For the most recent prescribing information, please visit www.pfizer.com.

For medical information about NIVESTYM, please visit www.pfizermedinfo.com or call 1-800-438-1985.

Manufactured by:
Hospira, Inc.,
a Pfizer Company
Lake Forest, IL 60045 USA
US License No. 1974

Distributed by Pfizer Labs,
division of Pfizer Inc.,
New York, NY 10001 USA

BD UltraSafe Plus is a trademark of Becton Dickinson and Company.

LAB-0933-10.0

Patient Information
NIVESTYM (Neye-ves-tim)
(filgrastim-aafi)
injection

What is NIVESTYM?

NIVESTYM is a man-made form of granulocyte colony-stimulating factor (G-CSF). G-CSF is a substance produced by the body. It stimulates the growth of neutrophils, a type of white blood cell important in the body's fight against infection.

Do not take NIVESTYM if you have had a serious allergic reaction to human G-CSFs such as filgrastim products or pegfilgrastim products.

Before you take NIVESTYM, tell your healthcare provider about all of your medical conditions, including if you:

- have a sickle cell disorder.
- have kidney problems.
- are receiving radiation therapy.
- are pregnant or plan to become pregnant. It is not known if NIVESTYM will harm your unborn baby.
- are breastfeeding or plan to breastfeed. It is not known if NIVESTYM passes into your breast milk.

Tell your healthcare provider about all the medicines you take, including prescription and over-the-counter medicines, vitamins, and herbal supplements.

How will I receive NIVESTYM?

- NIVESTYM injections can be given by a healthcare provider by intravenous (IV) infusion or under your skin (subcutaneous injection). Your healthcare provider may decide subcutaneous injections can be given at home by you or your caregiver. If NIVESTYM is given at home, see the detailed "Instructions for Use" that comes with your NIVESTYM for information on how to prepare and inject a dose of NIVESTYM.
- You and your caregiver should be shown how to prepare and inject NIVESTYM before you use it, by your healthcare provider.
- You should not try to inject a dose of NIVESTYM less than 0.3 mL (180 mcg) from a NIVESTYM prefilled syringe. A dose less than 0.3 mL cannot be accurately measured using the NIVESTYM prefilled syringe.
- Your healthcare provider will tell you how much NIVESTYM to inject and when to inject it. Do not change your dose or stop NIVESTYM unless your healthcare provider tells you to.
- If you are receiving NIVESTYM because you are also receiving chemotherapy, your dose of NIVESTYM should be injected at least 24 hours before or 24 hours after your dose of chemotherapy. Your healthcare provider will do blood tests to monitor your white blood cell count, and if necessary, adjust your NIVESTYM dose.
- If you miss a dose of NIVESTYM, talk to your healthcare provider about when you should give your next dose.

What are the possible side effects of NIVESTYM?

NIVESTYM may cause serious side effects, including:

- Spleen rupture. Your spleen may become enlarged and can rupture. A ruptured spleen can cause death. Call your healthcare provider right away if you have pain in the left upper stomach (abdomen) area or your left shoulder.
- A serious lung problem called acute respiratory distress syndrome (ARDS). Call your healthcare provider or get emergency medical help right away if you have shortness of breath with or without a fever, trouble breathing, or a fast rate of breathing.
- Serious allergic reactions. NIVESTYM can cause serious allergic reactions. These reactions can cause a rash over your whole body, shortness of breath, wheezing, dizziness, swelling around your mouth or eyes, fast heart rate, and sweating. If you have any of these symptoms, stop using NIVESTYM and call your healthcare provider or get emergency medical help right away.
- Sickle cell crises. You may have a serious sickle cell crisis, which could lead to death, if you have a sickle cell disorder and receive NIVESTYM. Call your healthcare provider right away if you have symptoms of sickle cell crisis such as pain or difficulty breathing.
- Kidney injury (glomerulonephritis). NIVESTYM can cause kidney injury. Call your healthcare provider right away if you develop any of the following symptoms:
  - swelling of your face or ankles
  - blood in your urine or dark colored urine
  - you urinate less than usual
- Capillary leak syndrome. NIVESTYM can cause fluid to leak from blood vessels into your body's tissues. This condition is called "Capillary Leak Syndrome" (CLS). CLS can quickly cause you to have symptoms that may become life-threatening. Get emergency medical help right away if you develop any of the following symptoms:
  - swelling or puffiness and are urinating less than usual
  - trouble breathing
  - swelling of your stomach area (abdomen) and feeling of fullness
  - dizziness or feeling faint
  - a general feeling of tiredness
- Myelodysplastic syndrome (MDS) and acute myeloid leukemia (AML).
  - NIVESTYM may increase the risk of developing a precancerous condition called MDS or a type of blood cancer called AML in people who were born with low white blood cell counts (congenital neutropenia).
  - If you have breast cancer or lung cancer, when NIVESTYM is used with chemotherapy and radiation therapy, or with radiation therapy only, you may have an increased risk of developing MDS or AML.
  - Symptoms of MDS and AML may include tiredness, fever, and easy bruising or bleeding.
  - Call your healthcare provider if you develop any of these symptoms during treatment with NIVESTYM.
- Decreased platelet count (thrombocytopenia). Your healthcare provider will check your blood during treatment with NIVESTYM. Tell your healthcare provider if you have unusual bleeding or bruising during treatment with NIVESTYM. This could be a sign of decreased platelet counts, which may reduce the ability of your blood to clot.
- Increased white blood cell count (leukocytosis). Your healthcare provider will check your blood during treatment with NIVESTYM.
- Inflammation of your blood vessels (cutaneous vasculitis). Tell your healthcare provider right away if you develop purple spots or redness of your skin.
- Inflammation of the aorta (aortitis). Inflammation of the aorta (the large blood vessel which transports blood from the heart to the body) has been reported in patients who received NIVESTYM. Symptoms may include fever, abdominal pain, feeling tired, and back pain. Call your healthcare provider if you experience these symptoms.

The most common side effects experienced in patients receiving NIVESTYM include:

- Patients with cancer receiving chemotherapy: fever, pain, rash, cough, and shortness of breath
- Patients with acute myeloid leukemia receiving chemotherapy: pain, nose bleed, and rash
- Patients with cancer receiving chemotherapy followed by bone marrow transplant: rash
- Patients who are having their own blood cells collected: bone pain, fever, and headache
- Patients with severe chronic neutropenia: pain, decreased red blood cells, nose bleed, diarrhea, reduced sensation, and hair loss

These are not all the possible side effects of NIVESTYM. Call your healthcare provider for medical advice about side effects. You may report side effects to FDA at 1-800-FDA-1088.

How should I store NIVESTYM?

- Store NIVESTYM in the refrigerator between 36°F to 46°F (2°C to 8°C).
- Do not freeze.
- Keep NIVESTYM in the original carton to protect from light or physical damage. Do not leave NIVESTYM in direct sunlight.
- Do not shake NIVESTYM.
- Take NIVESTYM out of the refrigerator 30 minutes before use and allow it to reach room temperature before preparing an injection.
- Throw away (dispose of) any NIVESTYM that has been left at room temperature for longer than 24 hours.
- After you inject your dose, throw away (dispose of) any unused NIVESTYM left in the vials or prefilled syringes. Do not save unused NIVESTYM in the vials or prefilled syringes for later use.

Keep NIVESTYM out of the reach of children.

General information about the safe and effective use of NIVESTYM.

Medicines are sometimes prescribed for purposes other than those listed in a Patient Information leaflet. Do not use NIVESTYM for a condition for which it was not prescribed. Do not give NIVESTYM to other people, even if they have the same symptoms that you have. It may harm them. You can ask your pharmacist or healthcare provider for information about NIVESTYM that is written for healthcare professionals.

What are the ingredients in NIVESTYM?

Active ingredient: (filgrastim-aafi)

Inactive ingredients: acetate, polysorbate 80, sodium, sorbitol, and water for Injection

Manufactured by Hospira, Inc., a Pfizer Company, Lake Forest, IL 60045 USA
US License No. 1974

Distributed by Pfizer Labs, division of Pfizer Inc., New York, NY 10001 USA

LAB-0935-5.0
For more information go to www.pfizer.com or call 1-800-438-1985.

This Patient Information has been approved by the U.S. Food and Drug Administration Revised: March 2023

Instructions for Use
NIVESTYM (Neye-ves-tim)
(filgrastim-aafi)
injection
Single-Dose Prefilled Syringe

Important

Read the Patient Information for important information you need to know about NIVESTYM before using this Instructions for Use.

Before you use a NIVESTYM prefilled syringe, read this important information.

Storing your prefilled syringe

- Store the NIVESTYM prefilled syringe in the refrigerator between 36˚F to 46˚F (2˚C to 8˚C).
- Do not freeze.
- Keep the NIVESTYM prefilled syringe in the original carton to protect from light or physical damage.
- Take the prefilled syringe out of the refrigerator 30 minutes before use and allow it to reach room temperature before preparing an injection.
- The NIVESTYM prefilled syringe may be allowed to reach room temperature for up to 24 hours. Throw away (dispose of) any NIVESTYM prefilled syringe that has been left at room temperature for longer than 24 hours.
- After you inject your dose, throw away (dispose of) any unused NIVESTYM left in the prefilled syringe. Do not save unused NIVESTYM in the prefilled syringe for later use.
- Keep NIVESTYM and all medicines out of the reach of children.

Using your prefilled syringe

- It is important that you do not try to give the injection unless you or your caregiver has received training from your healthcare provider.
- You should not inject a dose of NIVESTYM less than 0.3 mL (180 mcg) from a NIVESTYM prefilled syringe. A dose less than 0.3 mL cannot be accurately measured using the NIVESTYM prefilled syringe.
- Make sure the name NIVESTYM appears on the carton and prefilled syringe label.
- Do not use a NIVESTYM prefilled syringe after the expiration date on the label.
- Do not shake the NIVESTYM prefilled syringe.
- The prefilled syringe has a needle guard that needs to be activated to cover the needle after the injection is given. The needle guard will help prevent needle stick injuries to anyone who handles the prefilled syringe.
- Do not remove the needle cover from the prefilled syringe until you are ready to inject.
- Do not use the NIVESTYM prefilled syringe if the needle cover is missing.
- Do not use the prefilled syringe if the carton is open or damaged.
- Do not use a prefilled syringe if it has been dropped on a hard surface. The prefilled syringe may be broken even if you cannot see the break. Use a new prefilled syringe.

Call your healthcare provider if you have any questions.

About the NIVESTYM prefilled syringe
- NIVESTYM prefilled syringes come in two strengths. Depending on your prescription, you will receive NIVESTYM prefilled syringes that contain 300 mcg/0.5 mL or 480 mcg/0.8 mL of medicine. Your healthcare provider will determine the dose in milliliters (mL) that you will need to give based on your body weight.
- When you receive your NIVESTYM prefilled syringes, always check to see that the:
  - name NIVESTYM appears on the carton and prefilled syringe label.
  - expiration date on the prefilled syringe label has not passed. You should not use a prefilled syringe after the date on the label.
  - strength of NIVESTYM (number of micrograms on the carton containing the prefilled syringe) is the same as what your healthcare provider prescribed.
NIVESTYM prefilled syringe parts (see Figure A).
NIVESTYM 300 mcg/0.5 mL prefilled syringe is shown as an example.
Figure A
What you need for your injection
Included in the carton:
- 1 new NIVESTYM prefilled syringe (see Figure A above)
Not included in the carton (see Figure B)
- 1 adhesive bandage
- 1 alcohol wipe
- 1 cotton ball or gauze
- sharps disposal container
Figure B
Preparing the NIVESTYM prefilled syringe
Step 1: | Find a clean, well-lit flat work surface.
Step 2: | Take the carton containing the NIVESTYM prefilled syringe out of the refrigerator and leave it unopened on your work surface for at least 30 minutes so that it reaches room temperature. Put the original carton with any unused prefilled syringes back in the refrigerator.; - Do not shake the prefilled syringe. - Do not leave the prefilled syringe in direct sunlight.
Step 3: | Wash your hands with soap and water.
Step 4: | Remove the prefilled syringe from the carton by the needle guard only. Do not remove the prefilled syringe by its plunger or needle cover. See Figure C. Check to make sure that the needle guard is covering the barrel of the prefilled syringe.
Step 4: | Figure C
Step 4: | Do not push the needle guard over the needle cover before the injection. This may activate or lock the needle guard. See Figure D that shows a needle guard that has not yet been activated. This is how the prefilled syringe looks before use.
Step 4: | Figure D
Step 4: | If the needle guard is covering the needle that means it has been activated. See Figure E that shows a needle guard that has been activated. This is how the prefilled syringe looks after use. Do not use the NIVESTYM prefilled syringe. Get another prefilled syringe that has not been activated and is ready to use.
Step 4: | Figure E
Step 5: | Check the expiration date on the NIVESTYM prefilled syringe. Do not use the NIVESTYM prefilled syringe if the expiration date has passed.
Step 6: | Inspect the medicine and prefilled syringe. Turn the prefilled syringe so you can see the medicine and markings in the window. Make sure that you look at the medicine only through the viewing window on the prefilled syringe (see Figure F). Do not inspect the medicine through the plastic of the needle guard. Make sure the medicine in the prefilled syringe is clear and colorless.
Step 6: | Figure F
Step 6: | - Do not use the prefilled syringe if: - The medicine is cloudy or discolored or contains flakes or particles. - Any part of the prefilled syringe appears cracked or broken. - The prefilled syringe has been dropped. - The needle cover is missing or not securely attached. - The expiration date printed on the label has passed. - In all cases, use a new prefilled syringe and call your healthcare provider.
Step 7: | Choose the injection site; - When giving your injections, follow your healthcare provider's instructions about changing the site for each injection. - Areas of your body that you may use as injection sites include (see Figure G): - front of your thigh - stomach area (abdomen), except for a 2-inch area around your navel (belly button) - outer area of upper arm, only if a caregiver is giving you the injection - upper outer area of your buttocks, only if a caregiver is giving you the injection
 | Figure G
 | - Choose a different site for each injection of NIVESTYM. - Do not inject into areas where the skin is tender, bruised, red, or hard. Avoid injecting into areas with scars or stretch marks.
Step 8: | Clean your injection site with an alcohol wipe. See Figure H.; - Let your skin dry. - Do not touch this area again before injecting.
 | Figure H
Step 9: | Hold the prefilled syringe by the needle guard with the needle cover pointing up. Carefully pull the needle cover straight off and away from your body. Throw away the needle cover. Do not recap the needle. See Figure I.
 | Figure I
 | Your healthcare provider has prescribed either a "full" syringe dose or a "partial" syringe dose.; - If you are prescribed a partial dose of NIVESTYM, follow Steps 10 through 18. - If you are prescribed a full dose, you will inject all of the medicine from your prefilled syringe. For a full dose, skip Steps 10 and 11, and follow Steps 12 through 18.
Partial dosing
Step 10: | Point the needle up and tap gently until the air rises to the top. See Figure J.
 | Figure J
Step 11: | Holding the prefilled syringe as shown, slowly push up on the plunger rod to push out the extra air and medicine until the end of the conical base (edge) of the plunger stopper lines up with the syringe marking for your prescribed dose. See Figure K for an example of a dose of 0.3 mL. Your dose may be different than the example shown. Be careful not to activate the needle guard before use. Do not use a NIVESTYM prefilled syringe that has been activated. See Figure E above. Check again to make sure the correct dose of NIVESTYM is in the prefilled syringe.
 | Figure K
Giving the NIVESTYM prefilled syringe injection
Step 12: | With one hand, gently pinch a fold of skin at the injection site. Hold the pinch. See Figure L.
 | Figure L
Step 13: | With your other hand, hold the prefilled syringe like you would hold a pencil. Use a quick "dart-like" motion to insert the needle at a 45 to 90 degree angle into the skin as shown. See Figure M.
 | Figure M
Step 14: | Using slow and constant pressure, press down on the plunger rod until it reaches the bottom. See Figure N.
 | Figure N
Step 15: | Keep the plunger rod fully pressed down while you carefully pull the needle straight out from the injection site. See Figure O.
 | Figure O
Step 16: | As you let go of the plunger rod, the needle guard will automatically slide over the needle until the needle is completely covered and the needle guard locks into place. Do not recap the needle. See Figure P.
 | Figure P
Step 17: | There may be a small amount of blood at the injection site. You can press a cotton ball or gauze over the injection site and hold it for 10 seconds. Do not rub the injection site. You may cover the injection site with a small adhesive bandage, if needed. See Figure Q.
 | Figure Q
Step 18: | Throw away (dispose of) the syringe as instructed by your healthcare provider or by following the instructions below. See Figure R.
 | Figure R
Disposing of (throw away) used NIVESTYM prefilled syringes

- Put the used prefilled syringe in a FDA-cleared sharps disposal container right away after use. Do not throw away (dispose of) prefilled syringes in your household trash.
- If you do not have a FDA-cleared sharps disposal container, you may use a household container that is:
  - made of a heavy-duty plastic,
  - can be closed with a tight-fitting, puncture-resistant lid, without sharps being able to come out,
  - upright and stable during use,
  - leak-resistant, and
  - properly labeled to warn of hazardous waste inside the container.
- When your sharps disposal container is almost full, you will need to follow your community guidelines for the right way to dispose of your sharps disposal container. There may be state or local laws about how you should throw away used needles and syringes. For more information about safe sharps disposal, and for specific information about sharps disposal in the state that you live in, go to the FDA's website at: http://www.fda.gov/safesharpsdisposal.
- Do not dispose of your used sharps container in your household trash unless your community guidelines permit this. Do not recycle your used sharps disposal container.

This Instructions for Use has been approved by the U.S. Food and Drug Administration.

Manufactured by:
Hospira, Inc.,
a Pfizer Company
Lake Forest, IL 60045 USA
US License No. 1974

Distributed by Pfizer Labs,
division of Pfizer Inc.,
New York, NY 10001 USA

LAB-0938-6.0

For more information go to www.pfizer.com or call 1-800-438-1985.

Revised: February 2024

Instructions for Use
NIVESTYM (Neye-ves-tim)
(filgrastim-aafi)
injection
Single-Dose Vial

Important

Read the Patient Information for important information you need to know about NIVESTYM before using these Instructions for Use.

Before you use a NIVESTYM vial, read this important information:

Storing your NIVESTYM vial

- Store the vial in the refrigerator between 36˚F to 46˚F (2˚C to 8˚C).
- Do not freeze.
- Keep the vial in the original carton to protect from light or physical damage.
- Take the vial out of the refrigerator 30 minutes before use and allow it to reach room temperature before preparing an injection.
- Throw away (dispose of) any vial that has been left at room temperature for longer than 24 hours.
- After you inject your dose, throw away (dispose of) any unused NIVESTYM left in the vial. Do not save unused NIVESTYM in the vial for later use.

Keep NIVESTYM and all medicines out of the reach of children.

Using your vial

- It is important that you do not try to give the injection unless you or your caregiver has received training from your healthcare provider.
- Make sure the name NIVESTYM appears on the carton and vial label.
- Only use the vial 1 time. Discard (throw away) the vial with any remaining NIVESTYM liquid.
- Do not use a vial after the expiration date on the label.
- Do not shake the vial.
- Do not use the vial if the medicine is cloudy or discolored or contains flakes or particles.

Call your healthcare provider if you have any questions.

Step 1: Prepare

A. Remove the vial from the refrigerator.
  Find a clean, well-lit, flat work surface. Place the vial on your clean work surface for 30 minutes and allow it to reach room temperature before you give an injection.
  1. Do not try to warm the vial by using a heat source such as hot water or microwave.
  2. Do not leave the vial in direct sunlight.
  3. Do not shake the vial.
  4. Use the vial only 1 time.
B. Inspect the vial.
  Make sure the medicine in the vial is clear and colorless.
  1. Do not use the vial if:
    - The medicine is cloudy or discolored or contains flakes or particles.
    - The expiration date printed on the label has passed.
  2. In all cases, use a new vial and call your healthcare provider.
C. Gather all materials needed for your injection.
  Wash your hands thoroughly with soap and water. On your clean, well-lit, flat work surface, place:
  1. 1 Vial
  2. 1 Disposable syringe and needle
  3. 2 Alcohol wipes
  4. 1 Cotton ball or gauze pad
  5. 1 Adhesive bandage
  6. Sharps disposal container
  8. Only use the disposable syringes and needles that your healthcare provider prescribes.
  9. Only use the syringes and needles 1 time. Throw away (dispose of) any used syringes and needles. See Step 5 Finish, for instructions about how to properly dispose of used syringes and needles.
  10. You should only use a syringe that is marked in tenths of milliliters (mL).
  11. Your healthcare provider will show you how to measure the correct dose of NIVESTYM. This dose will be measured in milliliters (mL).

Step 2: Get Ready

D. Take the cap off the vial. Clean the rubber stopper with 1 alcohol wipe.
E. Check the carton containing the needle and syringe. If the carton has been opened or damaged, do not use that needle and syringe. Dispose of (throw away) that needle and syringe in the sharps disposal container.
F. Hold the syringe by the barrel with the needle cap pointing up. Carefully pull the needle cap straight off and away from your body.
Pull back on the plunger and draw air into the syringe that is the same amount (mL) as the dose of NIVESTYM that your healthcare provider prescribed.
  Important: Throw away the needle cap into the sharps disposal container. Do not recap the needle.
G. Keep the vial on the flat work surface and insert the needle straight down through the rubber stopper. Do not insert the needle through the rubber stopper more than 1 time.
H. Push the plunger down and inject all the air from the syringe into the vial of NIVESTYM.
I. Keep the needle in the vial and turn the vial upside down. Make sure that the NIVESTYM liquid is covering the tip of the needle.
J. Keep the vial upside down and slowly pull back on the plunger to fill the syringe barrel with NIVESTYM to the correct marking amount (mL) of medicine that matches the dose your healthcare provider prescribed.
K. Keep the needle in the vial and check for air bubbles in the syringe. If there are air bubbles, gently tap the syringe barrel with your finger until the air bubbles rise to the top. Slowly push the plunger up to push the air bubbles out of the syringe.
L. Keep the tip of the needle in the liquid and again pull the plunger back to the number on the syringe barrel that matches your dose. Check again for air bubbles. The air in the syringe will not hurt you, but too large an air bubble can reduce your dose of NIVESTYM. If there are still air bubbles, repeat the steps above to remove them.
M. Check again to make sure that you have the correct dose in the syringe. It is important that you use the exact dose prescribed by your healthcare provider. Do not remove the needle from the vial. Lay the vial down on its side with the needle still in the vial.

Step 3: Select and Prepare the Injection Site

N. Prepare and clean your injection site.
You can use:
  - Thigh
  - Stomach area (abdomen), except for a 2-inch area right around your navel (belly button)
  - Upper outer area of your buttocks (only if someone else is giving you the injection)
  - Outer area of upper arm (only if someone else is giving you the injection)
    Clean your injection site with a clean alcohol wipe.
    Let your skin dry.
  - Do not touch this area again before injecting.
  - If you want to use the same injection site, make sure it is not the same spot on the injection site area you used for a previous injection.
  - Do not inject into areas where the skin is tender, bruised, red, or hard. Avoid injecting into areas with scars or stretch marks.

Step 4: Subcutaneous (under the skin) injection

O. Remove the prepared syringe and needle from the vial.
P. Pinch your injection site to create a firm surface.
  Important: Keep skin pinched while injecting.
Q. Hold the pinch. Insert the needle into the skin at a 45 to 90 degree angle.
R. Using slow and constant pressure, push the plunger until it reaches the bottom.
  When done gently pull the needle out of the injection site at the same 45 to 90 degree angle used to insert it.

Step 5: Finish

S. Dispose of (throw away) the used needle and syringe.
  1. Put your used needles and syringes in a FDA-cleared sharps disposal container right away after use. Do not throw away (dispose of) loose needles, and syringes in your household trash.
  2. If you do not have a FDA-cleared sharps disposal container, you may use a household container that is:
    - made of a heavy-duty plastic,
    - can be closed with a tight-fitting, puncture-resistant lid, without sharps being able to come out,
    - upright and stable during use,
    - leak-resistant, and
    - properly labeled to warn of hazardous waste inside the container.
  3. When your sharps disposal container is almost full, you will need to follow your community guidelines for the right way to dispose of your sharps disposal container. There may be state or local laws about how you should throw away used needles and syringes. For more information about safe sharps disposal, and for specific information about sharps disposal in the state that you live in, go to the FDA's website at: http://www.fda.gov/safesharpsdisposal.
  4. Do not dispose of your used sharps disposal container in your household trash unless your community guidelines permit this. Do not recycle your used sharps disposal container.
T. Examine the injection site.
  If there is blood, press a cotton ball or gauze pad on your injection site. Do not rub the injection site. Apply an adhesive bandage if needed.

This Instructions for Use has been approved by the U.S. Food and Drug Administration.

Manufactured by:
Hospira, Inc.,
a Pfizer Company
Lake Forest, IL 60045 USA
US License No. 1974

Distributed by Pfizer Labs,
division of Pfizer Inc.,
New York, NY 10001 USA

LAB-0937-5.0
For more information go to www.pfizer.com or call 1-800-438-1985.

Revised: August 2023

PRINCIPAL DISPLAY PANEL - 1 mL Vial Label

NDC 0069-0293-01
Rx Only

Nivestym™
(filgrastim-aafi) Injection

300 mcg/mL

1 mL Single-Dose Vial

Pfizer

PRINCIPAL DISPLAY PANEL - 1 mL Vial Carton

10 x 300 mcg/mL Single-Dose Vials (containing 1 mL)
Discard unused portion

NDC 0069-0293-10
Rx Only

Nivestym™
(filgrastim-aafi) Injection

300 mcg/mL

A recombinant Granulocyte Colony Stimulating Factor (rG-CSF) derived from E. coli

For Intravenous or Subcutaneous Use Only

Sterile Solution - No Preservative

Pfizer
Oncology

PRINCIPAL DISPLAY PANEL - 1.6 mL Vial Label

NDC 0069-0294-01
Rx Only

Nivestym™
(filgrastim-aafi) Injection

480 mcg/1.6 mL
(300 mcg/mL)

1.6 mL Single-Dose Vial

Pfizer

PRINCIPAL DISPLAY PANEL - 1.6 mL Vial Carton

10 x 480 mcg/1.6 mL Single-Dose Vials (containing 1.6 mL)
Discard unused portion

NDC 0069-0294-10
Rx Only

Nivestym™
(filgrastim-aafi) Injection

480 mcg/1.6 mL (300 mcg/mL)

A recombinant Granulocyte Colony Stimulating Factor (rG-CSF) derived from E. coli

For Intravenous or Subcutaneous Use Only

Sterile Solution - No Preservative

Pfizer
Oncology

PRINCIPAL DISPLAY PANEL - 0.5 mL Syringe Label

NDC 0069-0291-01
Rx Only

Nivestym™
(filgrastim-aafi) Injection

300 mcg/0.5 mL

Single-Dose Prefilled Syringe with
Needle Guard
For Subcutaneous Use Only
Mfd by Hospira Inc, a Pfizer Company,
Lake Forest, IL 60045 USA

US License No. 1974

PRINCIPAL DISPLAY PANEL - 0.5 mL Syringe Carton

1 x 300 mcg/0.5 mL
Single-Dose Prefilled
Syringe with Needle
Guard

Discard unused portion.

Refrigerate at 2° to 8°C
(36° to 46°F). Do Not
Freeze or Shake. Protect
from light.

Subcutaneous
Use Only

Nivestym™
(filgrastim-aafi) Injection

300 mcg/0.5 mL

A recombinant Granulocyte Colony Stimulating
Factor (rG-CSF) derived from E. coli

Pfizer
Oncology

NDC 0069-0291-01
Rx Only

The syringe
plunger stopper
and needle cover
are not made with
natural rubber
latex.

Sterile Solution -
No Preservative

PRINCIPAL DISPLAY PANEL - 0.5 mL Syringe Carton - NDC 0069-0291-10

NDC 0069-0291-10
Rx Only

Nivestym™
(filgrastim-aafi) Injection

300 mcg/0.5 mL

10 x 300 mcg/0.5 mL
Single-Dose Prefilled Syringe with Needle Guard
Discard unused portion.

A recombinant Granulocyte Colony Stimulating Factor (rG-CSF) derived from E. coli

Subcutaneous Use Only
Sterile Solution - No Preservative

Pfizer
Oncology

PRINCIPAL DISPLAY PANEL - 0.5 mL Syringe Carton - NDC 0069-0291-01

NDC 0069-0291-01
Rx Only

Nivestym™
(filgrastim-aafi) Injection

300 mcg/0.5 mL

A recombinant Granulocyte Colony Stimulating
Factor (rG-CSF) derived from E. coli

1 x 300 mcg/0.5 mL
Single-Dose Prefilled Syringe with Needle Guard
Discard unused portion.

Subcutaneous Use Only
Sterile Solution - No Preservative

Pfizer
Oncology

PRINCIPAL DISPLAY PANEL - 0.8 mL Syringe Label

NDC 0069-0292-01
Rx Only

Nivestym™
(filgrastim-aafi) Injection

480 mcg/0.8 mL

Single-Dose Prefilled Syringe with
Needle Guard
For Subcutaneous Use Only
Mfd by Hospira Inc, a Pfizer Company,
Lake Forest, IL 60045 USA

US License No. 1974

PRINCIPAL DISPLAY PANEL - 0.8 mL Syringe Carton

1 x 480 mcg/0.8 mL
Single-Dose Prefilled Syringe
with Needle Guard

Discard unused portion.

Refrigerate at 2° to 8°C
(36° to 46°F).
Do Not Freeze or Shake. Protect
from light.

Subcutaneous
Use Only

NDC 0069-0292-01
Rx Only

Nivestym™
(filgrastim-aafi) Injection

480 mcg/0.8 mL

A recombinant Granulocyte Colony Stimulating
Factor (rG-CSF) derived from E. coli

Pfizer
Oncology

The syringe
plunger
stopper and
needle cover
are not made
with natural
rubber latex.

Sterile
Solution -
No
Preservative

PRINCIPAL DISPLAY PANEL - 0.8 mL Syringe Carton - NDC 0069-0292-10

NDC 0069-0292-10
Rx Only

Nivestym™
(filgrastim-aafi) Injection

480 mcg/0.8 mL

10 x 480 mcg/0.8 mL
Single-Dose Prefilled Syringe with Needle Guard
Discard unused portion.

A recombinant Granulocyte Colony Stimulating Factor (rG-CSF) derived from E. coli

Subcutaneous Use Only
Sterile Solution - No Preservative

Pfizer
Oncology

PRINCIPAL DISPLAY PANEL - 0.8 mL Syringe Carton - NDC 0069-0292-01

NDC 0069-0292-01
Rx Only

Nivestym™
(filgrastim-aafi) Injection

480 mcg/0.8 mL

A recombinant Granulocyte Colony Stimulating
Factor (rG-CSF) derived from E. coli

1 x 480 mcg/0.8 mL
Single-Dose Prefilled Syringe with Needle Guard
Discard unused portion.

Subcutaneous Use Only
Sterile Solution - No Preservative

Pfizer
Oncology